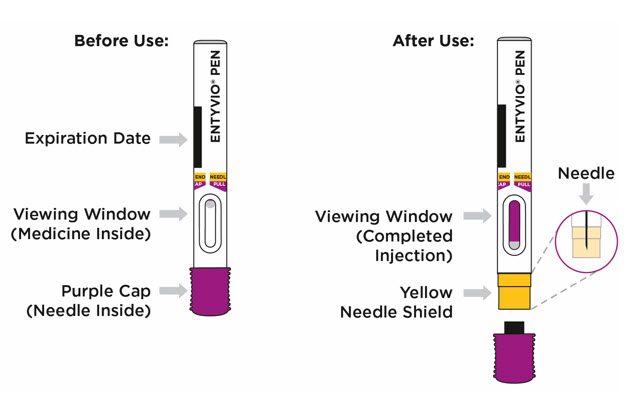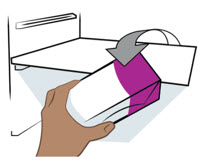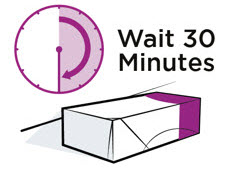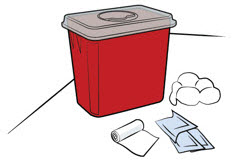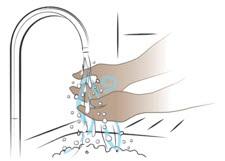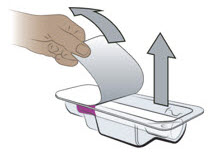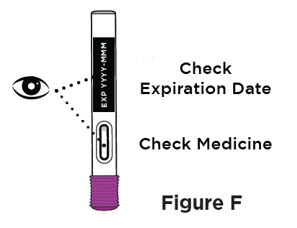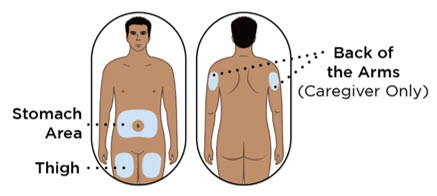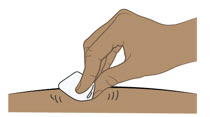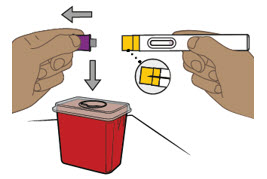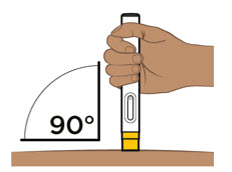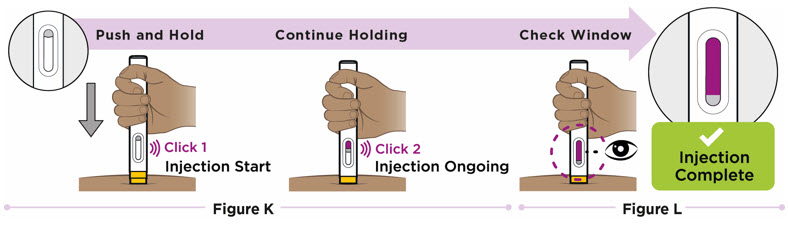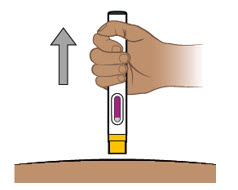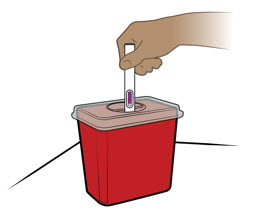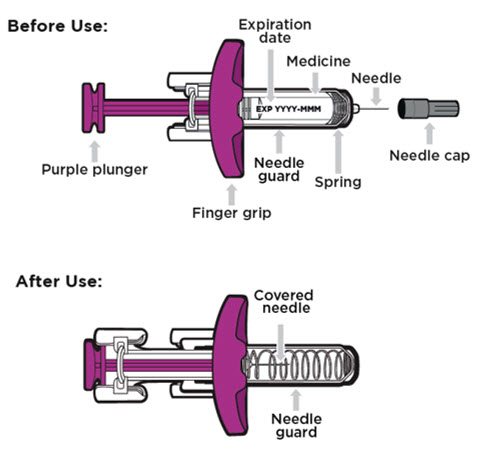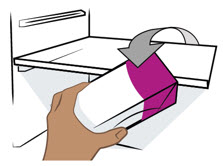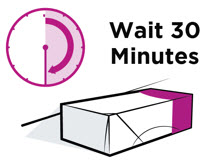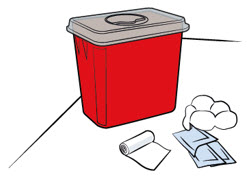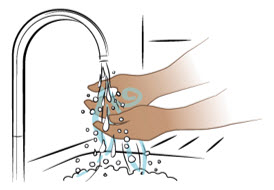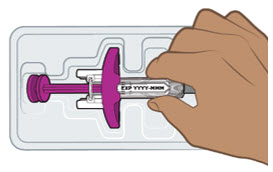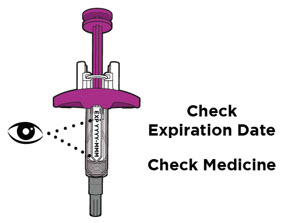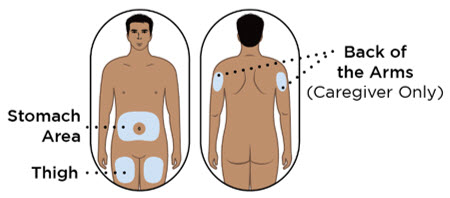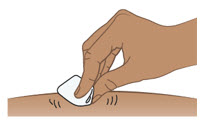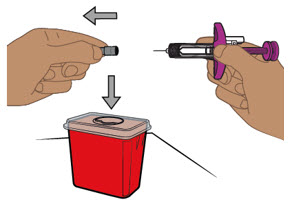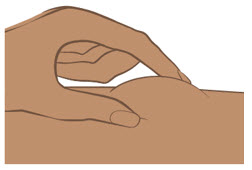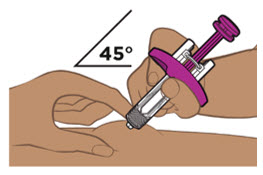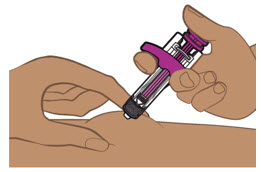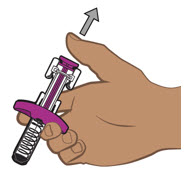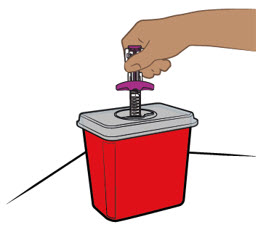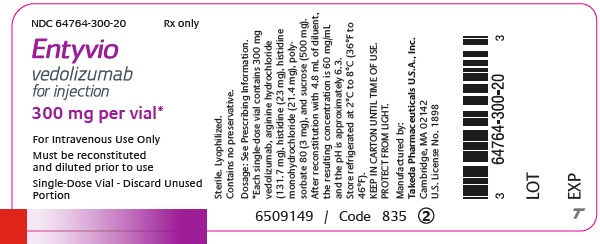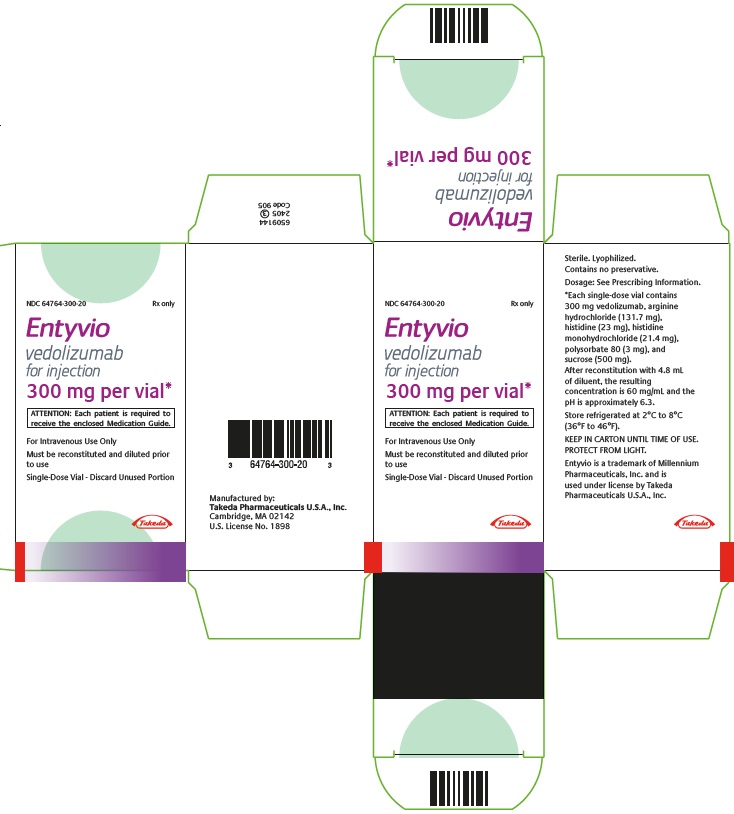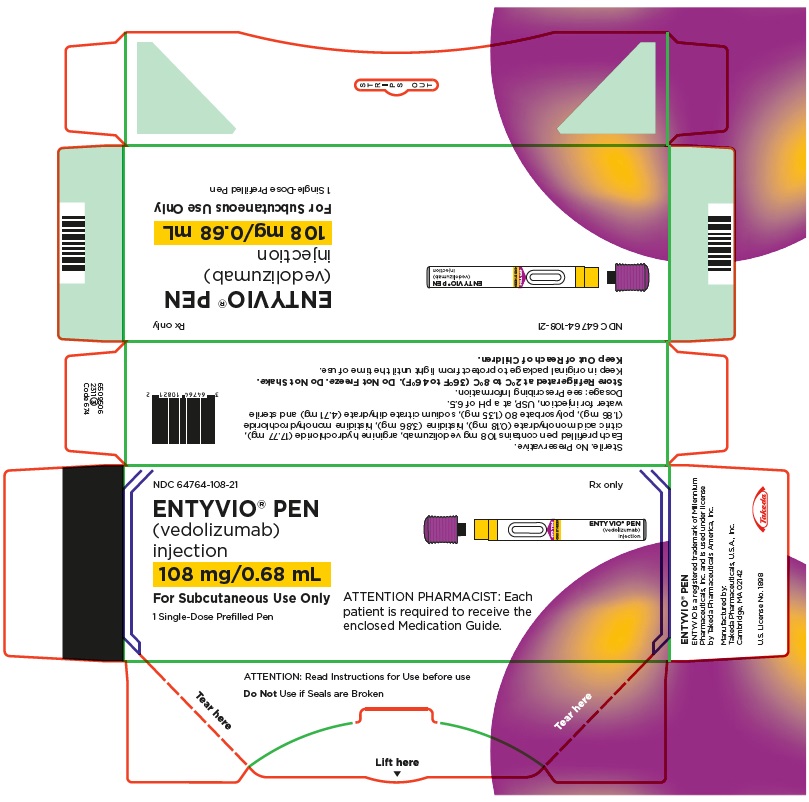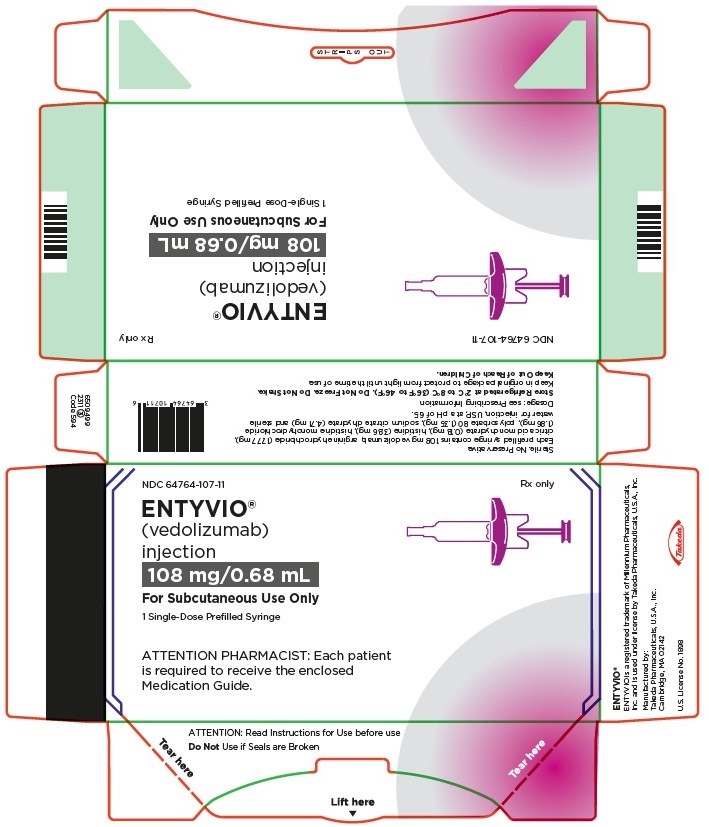 DRUG LABEL: Entyvio
NDC: 64764-300 | Form: INJECTION, POWDER, LYOPHILIZED, FOR SOLUTION
Manufacturer: Takeda Pharmaceuticals America, Inc.
Category: prescription | Type: HUMAN PRESCRIPTION DRUG LABEL
Date: 20260217

ACTIVE INGREDIENTS: VEDOLIZUMAB 300 mg/5 mL
INACTIVE INGREDIENTS: HISTIDINE 23 mg/5 mL; HISTIDINE MONOHYDROCHLORIDE 21.4 mg/5 mL; ARGININE HYDROCHLORIDE 131.7 mg/5 mL; SUCROSE 500 mg/5 mL; POLYSORBATE 80 3 mg/5 mL

HIGHLIGHTS OF PRESCRIBING INFORMATION

These highlights do not include all the information needed to use ENTYVIO® safely and effectively. See full prescribing information for ENTYVIO.
ENTYVIO (vedolizumab) for injection, for intravenous use
ENTYVIO (vedolizumab) injection, for subcutaneous use
ENTYVIO PEN (vedolizumab) injection, for subcutaneous use
Initial U.S. Approval: 2014

RECENT MAJOR CHANGES

Dosage and Administration Important Administration Information (2.1) | 9/2023
Recommended Dosage in Adults with Ulcerative Colitis and Crohn’s Disease (2.2) | 9/2023, 4/2024
Preparation and Administration Instructions for Subcutaneous Injection (2.4) | 4/2024

1 INDICATIONS AND USAGE

ENTYVIO is an integrin receptor antagonist indicated in adults for the treatment of:

- moderately to severely active ulcerative colitis (UC). (1)
- moderately to severely active Crohn's disease (CD). (1)

2 DOSAGE AND ADMINISTRATION

Important Administration Information

- Before initiating ENTYVIO, update immunizations according to current immunization guidelines. (2.1, 5.5)
- Intravenous Administration: ENTYVIO should be administered intravenously by a healthcare provider. (2.1)
- Subcutaneous Injection: ENTYVIO prefilled syringe and ENTYVIO PEN are intended for subcutaneous use. A patient may self-inject or caregiver may inject after proper training on correct subcutaneous injection technique. (2.1)

Recommended Dosage (2.2)

- Week 0: 300 mg infused intravenously over approximately 30 minutes.
- Week 2: 300 mg infused intravenously over approximately 30 minutes.
- Week 6: Patients may remain on ENTYVIO intravenous therapy or switch to subcutaneous injection after receiving two ENTYVIO intravenous doses administered at Week 0 and Week 2.
  - Intravenous Infusion: 300 mg infused over approximately 30 minutes and then every eight weeks thereafter.
  - Subcutaneous Injection: 108 mg subcutaneously once every two weeks.
- Discontinue ENTYVIO in patients who do not show evidence of therapeutic benefit by Week 14.
- Patients currently receiving and responding to ENTYVIO intravenous therapy after Week 6 may also be switched to subcutaneous injection. Administer the first subcutaneous dose in place of the next scheduled intravenous infusion and every two weeks thereafter.

Preparation and Administration Instructions:

- See full prescribing information for complete information on reconstitution, dilution, administration, and storage. (2.3, 2.4)

3 DOSAGE FORMS AND STRENGTHS

Intravenous infusion

- For injection: 300 mg vedolizumab in a single-dose vial. (3)

Subcutaneous injection

- Injection: 108 mg/0.68 mL solution in a single-dose prefilled syringe with needle safety device. (3)
- Injection: 108 mg/0.68 mL solution in a single-dose prefilled pen (ENTYVIO PEN). (3)

4 CONTRAINDICATIONS

Patients who have had a known serious or severe hypersensitivity reaction to ENTYVIO or any of its excipients. (4)

5 WARNINGS AND PRECAUTIONS

- Infusion-Related Reactions and Hypersensitivity Reactions: Discontinue ENTYVIO and initiate appropriate treatment if serious reactions occur. (5.1)
- Infections: Treatment with ENTYVIO is not recommended in patients with active, severe infections until the infections are controlled. Consider withholding ENTYVIO in patients who develop a severe infection while on treatment with ENTYVIO. (5.2)
- Progressive Multifocal Leukoencephalopathy (PML): Although unlikely, a risk of PML cannot be ruled out. Monitor patients for any new or worsening neurological signs or symptoms. (5.3)

6 ADVERSE REACTIONS

- Most common adverse reactions (incidence ≥3% and ≥1% higher than placebo) are: nasopharyngitis, headache, arthralgia, nausea, pyrexia, upper respiratory tract infection, fatigue, cough, bronchitis, influenza, back pain, rash, pruritus, sinusitis, oropharyngeal pain, and pain in extremities. (6.1)
  - Adverse reactions with subcutaneous ENTYVIO are similar to those reported with intravenous ENTYVIO with the exception of injection site reactions reported with subcutaneous ENTYVIO. (6.1)

To report SUSPECTED ADVERSE REACTIONS, contact Takeda Pharmaceuticals U.S.A., Inc. at 1-877-TAKEDA-7 (1-877-825-3327) or FDA at 1-800-FDA-1088 or www.fda.gov/medwatch.

FULL PRESCRIBING INFORMATION

1 INDICATIONS AND USAGE

ENTYVIO is indicated in adults for the treatment of:

- moderately to severely active ulcerative colitis (UC).
- moderately to severely active Crohn's disease (CD).

2 DOSAGE AND ADMINISTRATION

2.1 Important Administration Information

Before initiating ENTYVIO, update immunizations according to current immunization guidelines [see Warnings and Precautions (5.5)].

Intravenous Administration

- ENTYVIO should be administered by a healthcare provider prepared to manage hypersensitivity reactions including anaphylaxis, if they occur [see Warnings and Precautions (5.1)]. Appropriate monitoring and medical support measures should be available for immediate use. Observe patients during infusion and until the infusion is complete.
- Reconstitute and dilute ENTYVIO lyophilized powder prior to administration as a 30-minute intravenous infusion [see Dosage and Administration (2.3)].

Subcutaneous Injection

- ENTYVIO prefilled syringe and ENTYVIO PEN are intended for subcutaneous use under the guidance and supervision of a healthcare professional.
- Patients may self-inject or caregivers may inject subcutaneous ENTYVIO using either the ENTYVIO prefilled syringe or ENTYVIO PEN after training in subcutaneous injection technique. Provide proper training to patients and/or caregivers on the subcutaneous injection technique of ENTYVIO.

2.2 Recommended Dosage in Adults with Ulcerative Colitis and Crohn’s Disease

- Week 0: Administer ENTYVIO 300 mg by intravenous infusion over approximately 30 minutes [see Dosage and Administration (2.3)].
- Week 2: Administer ENTYVIO 300 mg by intravenous infusion over approximately 30 minutes.
- Week 6: Patients may remain on ENTYVIO intravenous therapy or switch to subcutaneous injection after receiving two ENTYVIO intravenous doses administered at Week 0 and Week 2.
  - Intravenous Infusion: Administer ENTYVIO 300 mg by intravenous infusion over approximately 30 minutes and then every eight weeks thereafter.
  - Subcutaneous Injection: Administer ENTYVIO 108 mg subcutaneously once every 2 weeks.
- Discontinue therapy in patients who show no evidence of therapeutic benefit by Week 14.

Patients currently receiving and responding to ENTYVIO intravenous therapy after Week 6 may also be switched to subcutaneous injection. Administer the first subcutaneous dose in place of the next scheduled intravenous infusion and every two weeks thereafter.

2.3 Preparation and Administration Instructions for Intravenous Infusion

Reconstitution Instructions

1. Remove the flip-off cap from the single-dose vial and wipe with alcohol swab. Reconstitute ENTYVIO vial containing lyophilized powder with 4.8 mL of Sterile Water for injection, 0.9% Sodium Chloride Injection, or Lactated Ringer's Injection, at room temperature (20°C to 25°C [68ºF to 77ºF]), using a syringe with a 21- to 25-gauge needle.
2. Insert the syringe needle into the vial through the center of the stopper and direct the stream of Sterile Water for Injection, 0.9% Sodium Chloride Injection, or Lactated Ringer's Injection, to the glass wall of the vial to avoid excessive foaming.
3. Gently swirl the vial for at least 15 seconds to dissolve the lyophilized powder. Do not vigorously shake or invert.
4. Allow the solution to sit for up to 20 minutes at room temperature to allow for reconstitution and for any foam to settle; the vial can be swirled and inspected for dissolution during this time. If not fully dissolved after 20 minutes, allow another 10 minutes for dissolution. Do not use the vial if the drug product is not dissolved within 30 minutes.
5. Visually inspect the reconstituted ENTYVIO solution for particulate matter and discoloration prior to dilution. Solution should be clear or opalescent, colorless to light brownish yellow and free of visible particulates. Do not administer reconstituted solution showing uncharacteristic color or containing particulates.
6. Once dissolved, gently invert vial three times.
7. Immediately, withdraw 5 mL (300 mg) of reconstituted ENTYVIO solution using a syringe with a 21- to 25-gauge needle. Discard any remaining portion of the reconstituted solution in the vial.

Dilution Instructions

Add the 5 mL (300 mg) of reconstituted ENTYVIO solution to 250 mL of 0.9% Sodium Chloride Injection, or Lactated Ringer's Injection, and gently mix the infusion bag. Do not add other medicinal products to the prepared infusion solution or intravenous infusion set. Once reconstituted and diluted, use the infusion solution as soon as possible.

Discard any unused portion of the infusion solution.

Administration Instructions

After the infusion is complete, flush with 30 mL of 0.9% Sodium Chloride Injection, or Lactated Ringer's Injection.

Storage and Stability

Specific storage conditions and timing for the reconstituted solution in vial and diluted solution in the infusion bag are outlined in Table 1.

Do not freeze the reconstituted solution in the vial or the diluted solution in the infusion bag.

Table 1. Storage Instructions for Reconstituted Solution in Vial and Diluted Solution in Infusion Bag
Solution | Storage Conditions
Solution | Refrigeration (2°C to 8°C [36°F to 46°F]) | Room Temperature (20°C to 25°C [68°F to 77°F])
Reconstituted Solution (in Sterile Water for Injection, 0.9% Sodium Chloride Injection, or Lactated Ringer's Injection, inside vial) | 8 hours | Use immediately after reconstitution
Diluted Solution (in 0.9% Sodium Chloride Injection) | 24 hours [This time assumes the reconstituted solution is immediately diluted in the 0.9% Sodium Chloride Injection, or Lactated Ringer's Injection, and held in the infusion bag only. Any time that the reconstituted solution was held in vial should be subtracted from the time the solution may be held in the infusion bag.] , [This period may include up to 12 hours at room temperature (20°C to 25°C [68°F to 77°F]).] | 12 hours
Diluted Solution (in Lactated Ringer's Injection) | 6 hours | Use immediately after dilution

The combined storage time of reconstituted ENTYVIO solution in the vial and the diluted solution in the infusion bag with 0.9% Sodium Chloride Injection, is a total of 12 hours at room temperature (20°C to 25°C [68°F to 77°F]) or 24 hours refrigerated (2°C to 8°C [36°F to 46°F]). This combined storage time may include up to eight hours of the reconstituted solution in the vial at 2°C to 8°C.

The combined storage time of reconstituted ENTYVIO solution in the vial and the diluted solution in the infusion bag with Lactated Ringer's Injection, is a total of six hours refrigerated (2°C to 8°C [36°F to 46°F]).

2.4 Preparation and Administration Instructions for Subcutaneous Injection

- Inspect the solution visually for particulate matter and discoloration prior to administration. ENTYVIO in prefilled syringe or ENTYVIO PEN should be a clear to moderately opalescent, colorless to slightly yellow solution. Do not use ENTYVIO prefilled syringes or ENTYVIO PENs with visible particulate matter or discoloration.
- Administer each subcutaneous injection at a different anatomic location (such as thighs, any quadrant of abdomen, or upper arms) than the previous injection. Administration of ENTYVIO in the back of upper arm may only be performed by a healthcare professional or caregiver. Do not inject into moles, scars, bruises, or areas where the skin is tender, erythematous, or indurated.

Missed Subcutaneous Dose

If treatment with subcutaneous ENTYVIO is interrupted or if a scheduled dose(s) of subcutaneous ENTYVIO is missed, inject the next subcutaneous dose as soon as possible and then every 2 weeks thereafter.

In the event of incomplete dose administration (i.e., patient attempts administration of dose with ENTYVIO PEN, however it is uncertain if a full dose was administered), instruct the patient to call their pharmacy or healthcare provider.

3 DOSAGE FORMS AND STRENGTHS

Intravenous Infusion

- For injection: 300 mg of vedolizumab as a white to off-white lyophilized cake in a single-dose vial for reconstitution.

Subcutaneous Injection

- Injection: 108 mg/0.68 mL vedolizumab as a clear to moderately opalescent, colorless to slightly yellow solution in a single-dose prefilled syringe with needle safety device.
- Injection: 108 mg/0.68 mL vedolizumab as a clear to moderately opalescent, colorless to slightly yellow solution in a single-dose prefilled pen (ENTYVIO PEN).

4 CONTRAINDICATIONS

ENTYVIO is contraindicated in patients who have had a known serious or severe hypersensitivity reaction to ENTYVIO or any of its excipients (such as dyspnea, bronchospasm, urticaria, flushing, rash and increased heart rate) [see Warnings and Precautions (5.1)].

5 WARNINGS AND PRECAUTIONS

5.1 Infusion-Related Reactions and Hypersensitivity Reactions

Infusion-related reactions and hypersensitivity reactions have been reported, including anaphylaxis, dyspnea, bronchospasm, urticaria, flushing, rash, and increased blood pressure and heart rate [see Adverse Reactions (6.1, 6.2)]. These reactions may occur with the first or subsequent infusions of ENTYVIO and may vary in their time of onset from during infusion or up to several hours post-infusion.

If anaphylaxis or other serious infusion-related or hypersensitivity reactions occur, discontinue administration of ENTYVIO immediately and initiate appropriate treatment.

5.2 Infections

Patients treated with ENTYVIO are at increased risk for developing infections [see Adverse Reactions (6.1)]. The most commonly reported infections in clinical trials occurring at a rate greater on ENTYVIO than placebo involved the upper respiratory and nasal mucosa (e.g., nasopharyngitis, upper respiratory tract infection). Serious infections have also been reported in patients treated with ENTYVIO, including anal abscess, sepsis (some fatal), tuberculosis, salmonella sepsis, Listeria meningitis, giardiasis and cytomegaloviral colitis.

ENTYVIO is not recommended in patients with active, severe infections until the infections are controlled. Consider withholding treatment in patients who develop a severe infection while on treatment with ENTYVIO. Exercise caution when considering the use of ENTYVIO in patients with a history of recurring severe infections. Consider screening for tuberculosis (TB) according to the local practice. For progressive multifocal leukoencephalopathy (PML), [see Warnings and Precautions (5.3)].

5.3 Progressive Multifocal Leukoencephalopathy

PML, a rare and often fatal opportunistic infection of the central nervous system (CNS), has been reported with systemic immunosuppressants, including another integrin receptor antagonist. PML is caused by the John Cunningham (JC) virus and typically only occurs in patients who are immunocompromised. One case of PML in an ENTYVIO-treated patient with multiple contributory factors has been reported in the postmarketing setting (e.g., human immunodeficiency virus [HIV] infection with a CD4 count of 300 cells/mm^3 and prior and concomitant immunosuppression). Although unlikely, a risk of PML cannot be ruled out.

Monitor patients on ENTYVIO for any new onset, or worsening, of neurological signs and symptoms. Typical signs and symptoms associated with PML are diverse, progress over days to weeks, and include progressive weakness on one side of the body or clumsiness of limbs, disturbance of vision, and changes in thinking, memory, and orientation leading to confusion and personality changes. The progression of deficits usually leads to death or severe disability over weeks or months. If PML is suspected, withhold dosing with ENTYVIO and refer to a neurologist; if confirmed, discontinue dosing permanently.

5.4 Liver Injury

There have been reports of elevations of transaminase and/or bilirubin in patients receiving ENTYVIO. In general, the combination of transaminase elevations and elevated bilirubin without evidence of obstruction is generally recognized as an important predictor of severe liver injury that may lead to death or the need for a liver transplant in some patients. ENTYVIO should be discontinued in patients with jaundice or other evidence of significant liver injury [see Adverse Reactions (6.1)].

5.5 Live and Oral Vaccines

Prior to initiating treatment with ENTYVIO, all patients should be brought up to date with all immunizations according to current immunization guidelines [see Dosage and Administration (2.1)]. Patients receiving ENTYVIO may receive non-live vaccines (e.g., influenza vaccine injection) and may receive live vaccines if the benefits outweigh the risks. There are no data on the secondary transmission of infection by live vaccines in patients receiving ENTYVIO [see Adverse Reactions (6.1)].

6 ADVERSE REACTIONS

The following topics are also discussed in detail in the Warnings and Precautions section:

- Infusion-Related Reactions and Hypersensitivity Reactions [see Warnings and Precautions (5.1)]
- Infections [see Warnings and Precautions (5.2)]
- Progressive Multifocal Leukoencephalopathy [see Warnings and Precautions (5.3)]
- Liver Injury [see Warnings and Precautions (5.4)]

6.1 Clinical Trials Experience

Because clinical trials are conducted under widely varying conditions, adverse reaction rates observed in the clinical trials of a drug cannot be directly compared to rates in the clinical trials of another drug and may not reflect the rates observed in practice.

The data described below reflect exposure to intravenous ENTYVIO in 3,326 patients and healthy volunteers in clinical trials, including 1,396 exposed for greater than one year, and 835 exposed for greater than two years.

Intravenous Infusion

The safety data described in Table 2 are derived from four controlled Phase 3 trials (UC Trials I and II and CD Trials I and III); data from adult patients receiving open-label intravenous ENTYVIO treatment at Weeks 0 and 2 (prior to entry into UC Trial II and CD Trial III) and from Weeks 6 to 52 (non-responders at Week 6 of UC Trial I and CD Trial I) are included [see Clinical Studies (14.1, 14.2)].

In these trials, 1,434 patients received ENTYVIO 300 mg intravenously for up to 52 weeks, and 297 patients received placebo for up to 52 weeks. Of these, 769 patients had ulcerative colitis and 962 patients had Crohn's disease. Patients were exposed for a mean duration of 259 days (UC Trials I and II) and 247 days (CD Trials I and III).

Adverse reactions were reported in 52% of patients treated with intravenous ENTYVIO and 45% of patients treated with placebo (UC Trials I and II: 49% with ENTYVIO and 37% with placebo; CD Trials I and III: 55% with ENTYVIO and 47% with placebo). Serious adverse reactions were reported in 7% of patients treated with intravenous ENTYVIO compared to 4% of patients treated with placebo (UC Trials I and II: 8% with ENTYVIO and 7% with placebo; CD Trials I and III: 12% with ENTYVIO and 9% with placebo).

The most common adverse reactions (reported by ≥3% of patients treated with intravenous ENTYVIO in the UC Trials I and II and CD Trials I and III combined group and ≥1% higher than in combined placebo group) were nasopharyngitis, headache, arthralgia, nausea, pyrexia, upper respiratory tract infection, fatigue, cough, bronchitis, influenza, back pain, rash, pruritus, sinusitis, oropharyngeal pain, and pain in extremities (Table 2).

Table 2. Adverse Reactions in ≥3% of Intravenous ENTYVIO-Treated Adult Patients and ≥1% Higher than in Placebo (UC Trials I and II [Data from patients receiving open-label intravenous ENTYVIO treatment at Weeks 0 and 2 (prior to entry into UC Trial II and CD Trial III) and from Weeks 6 to 52 (non-responders at Week 6 of UC Trial I and CD Trial I) are included.] and CD Trials I and III)
Adverse Reaction | ENTYVIO IV [Patients who received ENTYVIO for up to 52 weeks.] (N=1434) | Placebo [Patients who received placebo for up to 52 weeks.] (N=297)
Nasopharyngitis | 13% | 7%
Headache | 12% | 11%
Arthralgia | 12% | 10%
Nausea | 9% | 8%
Pyrexia | 9% | 7%
Upper respiratory tract infection | 7% | 6%
Fatigue | 6% | 3%
Cough | 5% | 3%
Bronchitis | 4% | 3%
Influenza | 4% | 2%
Back pain | 4% | 3%
Rash | 3% | 2%
Pruritus | 3% | 1%
Sinusitis | 3% | 1%
Oropharyngeal pain | 3% | 1%
Pain in extremities | 3% | 1%

Safety data for patients (n=279) in UC Trials I and II and CD Trials I and III who received intravenous ENTYVIO at Weeks 0 and 2 and were then randomized to placebo at Week 6 for up to 52 weeks, and for patients (n=416) in CD Trial II, a 10-week Crohn's disease trial, are similar to those listed in Table 2.

Infusion-Related Reactions and Hypersensitivity Reactions

Serious infusion-related reactions and hypersensitivity reactions including anaphylaxis have been reported following intravenous ENTYVIO administration in clinical trials [see Warnings and Precautions (5.1)]. In UC Trials I and II and CD Trials I and III, one case of anaphylaxis [one out of 1,434 patients treated with intravenous ENTYVIO (0.07%)] was reported by a Crohn's disease patient during the second infusion (symptoms reported were dyspnea, bronchospasm, urticaria, flushing, rash, and increased blood pressure and heart rate) and was managed with discontinuation of infusion and treatment with antihistamine and intravenous hydrocortisone.

In UC Trials I and II and CD Trials I and III, 4% of patients treated with intravenous ENTYVIO and 3% of patients treated with placebo experienced an infusion-related reaction (IRR). The most frequently observed IRRs in the patients treated with intravenous ENTYVIO (reported more than twice) were nausea, headache, pruritus, dizziness, fatigue, infusion-related reaction, pyrexia, urticaria, and vomiting (each of these adverse reactions occurred in <1% in all patients treated with intravenous ENTYVIO) and no individual adverse reaction reported occurred at a rate above 1%. These reactions generally occurred within the first two hours after the infusion and resolved with no treatment or following antihistamine and/or IV hydrocortisone treatment. Less than 1% of patients treated with intravenous ENTYVIO had IRRs assessed by the investigator as severe, and IRRs requiring discontinuation of study treatment occurred in <1%.

In clinical trials, for patients with mild IRRs or hypersensitivity reactions, physicians were allowed to pretreat with standard medical treatment (e.g., antihistamine, hydrocortisone, and/or acetaminophen) prior to next infusion.

Infections

In UC Trials I and II and CD Trials I and III, the rate of infections was 0.85 per patient-year in the patients treated with intravenous ENTYVIO and 0.7 per patient-year in the patients treated with placebo [see Warnings and Precautions (5.2)]. The infections consisted primarily of nasopharyngitis, upper respiratory tract infection, sinusitis, and urinary tract infection. Two percent of patients discontinued intravenous ENTYVIO due to infections.

In UC Trials I and II and CD Trials I and III, the rate of serious infections was 0.07 per patient-year in patients treated with intravenous ENTYVIO and 0.06 per patient-year in patients treated with placebo. Serious infections were more common in Crohn's disease patients than ulcerative colitis patients, and anal abscesses were the most frequently reported serious adverse reaction in Crohn's disease patients. Over 48 months, there was no increase in the rate of serious infections.

In controlled- and open-label long-term extension trials in adults treated with intravenous ENTYVIO, serious infections have been reported, including anal abscess, sepsis (some fatal), tuberculosis, salmonella sepsis, Listeria meningitis, giardiasis, and cytomegaloviral colitis.

In UC Trials I and II and CD Trials I and III, sepsis, including bacterial sepsis and septic shock, was reported in four of 1,434 (0.3%) patients treated with intravenous ENTYVIO and in two of 297 patients treated with placebo (0.7%). During these trials, two Crohn's disease patients treated with intravenous ENTYVIO died due to reported sepsis or septic shock; both patients had significant comorbidities and a complicated hospital course that contributed to the deaths. In an open label, long-term extension trial, additional cases of sepsis (some fatal), including bacterial sepsis and septic shock, were reported. The rate of sepsis in patients with ulcerative colitis or Crohn's disease receiving intravenous ENTYVIO was two per 1,000 patient-years.

In clinical trials, all patients were screened for tuberculosis. One case of latent, pulmonary tuberculosis was diagnosed during the controlled trials with intravenous ENTYVIO. Additional cases of pulmonary tuberculosis were diagnosed during the open-label trial. All of these observed cases occurred outside the United States (U.S.), and none of the patients had extrapulmonary manifestations.

Liver Injury

There have been reports of elevations of transaminase and/or bilirubin in patients receiving intravenous ENTYVIO [see Warnings and Precautions (5.4)]. In UC Trials I and II and CD Trials I and III, three patients reported serious adverse reactions of hepatitis, manifested as elevated transaminases with or without elevated bilirubin and symptoms consistent with hepatitis (e.g., malaise, nausea, vomiting, abdominal pain, anorexia). These adverse reactions occurred following two to five intravenous ENTYVIO doses; however, based on case report information it is unclear if the reactions indicated drug-induced or autoimmune etiology. All patients recovered following discontinuation of therapy with some requiring corticosteroid treatment. In controlled trials, the incidence of ALT and AST elevations ≥3× ULN was <2% in patients treated with intravenous ENTYVIO and in patients treated with placebo. In the open-label trial, one additional case of serious hepatitis was observed.

Malignancies

In UC Trials I and II and CD Trials I and III, malignancies (excluding dysplasia and basal cell carcinoma) were reported in six of 1,434 (0.4%) patients treated with intravenous ENTYVIO, including colon cancer (n=2), transitional cell carcinoma (n=1), breast cancer (n=1), carcinoid tumor of the appendix (n=1), and squamous cell carcinoma (n=1). Malignancy was reported in one of 297 (0.3%) patients treated with placebo (squamous cell carcinoma).

Malignancies (excluding dysplasia and basal cell carcinoma) observed during the ongoing open-label long-term extension trial included B-cell lymphoma, breast cancer, colon cancer, malignant hepatic neoplasm, malignant lung neoplasm, malignant melanoma, lung cancer of primary neuroendocrine carcinoma, renal cancer, and squamous cell carcinoma. Overall, the number of malignancies in the clinical trials was small; however, long-term exposure was limited.

Subcutaneous Injection after Two Intravenous Doses of ENTYVIO

ENTYVIO was administered as a subcutaneous injection in adult patients with ulcerative colitis and Crohn’s disease in double-blind, placebo-controlled clinical trials (SC UC Trial and SC CD Trial, respectively). Patients who achieved clinical response following two doses of ENTYVIO administered as an intravenous infusion at Week 0 and Week 2 were randomized 2:1 at Week 6 to ENTYVIO as a subcutaneous injection (N=106) or placebo (N=56) (SC UC Trial) and as a subcutaneous injection (N=275) or placebo (N=134) (SC CD Trial) [see Clinical Studies (14.1, 14.2)].

The safety profile for up to 52 weeks of total treatment was similar between patients who were switched to ENTYVIO as a subcutaneous injection in SC UC and SC CD clinical trials and patients in UC and CD clinical trials who received ENTYVIO as an intravenous infusion (Table 2) except for injection site reactions, which were reported with subcutaneous ENTYVIO. Injection site reactions with subcutaneous ENTYVIO were reported in 10% (11/106) of patients in SC UC Trial, including injection site erythema, rash, pruritus, swelling, bruising, and hematoma. Injection site reactions with subcutaneous ENTYVIO were reported in 3% (8/275) of patients in SC CD Trial, including injection site erythema, pruritus, urticaria, pain, rash, and edema.

Live and Oral Vaccines

There are no data on the secondary transmission of infection by live vaccines in patients receiving ENTYVIO.

In a placebo-controlled study of healthy volunteers, 61 subjects were given a single intravenous ENTYVIO 750 mg dose (2.5 times the recommended dose), and 62 subjects received placebo followed by intramuscular vaccination with Hepatitis B surface antigen and oral cholera vaccine. After intramuscular vaccination with three doses of recombinant Hepatitis B surface antigen, those treated with intravenous ENTYVIO did not have lower rates of protective immunity to Hepatitis B virus. However, those exposed to intravenous ENTYVIO did have lower seroconversion rates and anti-cholera titers relative to placebo after receiving the two doses of a killed, oral cholera vaccine. The impact on other oral vaccines and on nasal vaccines in patients is unknown.

6.2 Postmarketing Experience

The following adverse reactions have been identified during post-approval use of ENTYVIO. Because these reactions are reported voluntarily from a population of uncertain size, it is not always possible to reliably estimate their frequency or establish a causal relationship to drug exposure.

Immune system disorders: Anaphylaxis [see Warnings and Precautions (5.1)].

Gastrointestinal system disorders: Acute pancreatitis.

Respiratory, thoracic, and mediastinal disorders: Interstitial lung disease, pneumonitis.

7 DRUG INTERACTIONS

7.1 Natalizumab Products

Because of the potential for increased risk of PML and other infections, avoid the concomitant use of ENTYVIO with natalizumab products.

7.2 TNF Blockers

Because of the potential for increased risk of infections, avoid the concomitant use of ENTYVIO with TNF blockers.

7.3 CYP450 Substrates

The formation of CYP450 enzymes may be suppressed by increased levels of certain cytokines (e.g., IL-6, IL-10, TNFα, IFN) during chronic inflammation. Therefore, use of ENTYVIO may normalize the formation of CYP450 enzymes by modulating the underlying disease. Upon initiation or discontinuation of ENTYVIO in patients treated with CYP450 substrates, monitor drug concentrations or other therapeutic parameters, and adjust the dosage of the CYP substrate as needed. See the prescribing information of specific CYP substrates.

8 USE IN SPECIFIC POPULATIONS

8.1 Pregnancy

Risk Summary

Available data from the Organization of Teratology Information Specialists (OTIS)/MotherToBaby ENTYVIO Pregnancy Registry, published literature and pharmacovigilance in pregnant women have not reliably identified an ENTYVIO-associated risk of major birth defects, miscarriage or adverse maternal or fetal outcomes (see Data). There are risks to the mother and the fetus associated with inflammatory bowel disease in pregnancy (see Clinical Considerations).

No fetal harm was observed in animal reproduction studies with intravenous administration of vedolizumab to rabbits and monkeys at dose levels 20 times the recommended human dosage (see Data).

The background risk of major birth defects and miscarriage for the indicated populations is unknown. All pregnancies have a background risk of birth defect, loss, or other adverse outcomes. In the U.S. general population, the estimated background risk of major birth defects and miscarriage in clinically recognized pregnancies is 2 to 4% and miscarriage is 15 to 20%, respectively.

Clinical Considerations

Disease-Associated Maternal and Embryo/Fetal Risk

Published data suggest that the risk of adverse pregnancy outcomes in women with inflammatory bowel disease (IBD) is associated with increased disease activity. Adverse pregnancy outcomes include preterm delivery (before 37 weeks of gestation), low birth weight (less than 2,500 g) infants, and small for gestational age at birth.

Fetal/Neonatal Adverse Reactions

ENTYVIO administered during pregnancy could affect immune responses in the in utero exposed newborn and infant. The clinical significance of low levels of ENTYVIO in utero-exposed infants is unknown. The safety of administering live or live-attenuated vaccines in exposed infants is unknown.

Data

Human Data

The vedolizumab pregnancy exposure registry conducted by OTIS/MotherToBaby study in the United States and Canada collected prospective observational data between 2015 and 2022 to assess the risk of major birth defects in live-born infants of women with ulcerative colitis (UC) or Crohn’s disease (CD) treated with vedolizumab during pregnancy. The study compared pregnant patients with UC or CD exposed to vedolizumab with pregnant patients with UC or CD treated with other biological products. The registry included 99 women (58 with UC, 41 with CD) treated with vedolizumab during pregnancy, and 76 women (27 with UC, 49 with CD) exposed to other biological products during pregnancy.

The proportion of major birth defects among live-born infants in patients with UC or CD treated with vedolizumab and patients with UC or CD treated with other biological products was 7.4% (7/94) and 5.6% (4/71), respectively. Overall, there was no evidence of increased risk for major structural birth defects (adjusted RR 1.07, 95% CI: 0.33, 3.52).

The methodological limitations of the registry, including small sample size and the non-randomized design, resulted in a limited ability to estimate the risk of major birth defects and other maternal and infant outcomes. The conclusions from the pregnancy registry were consistent with the published literature and pharmacovigilance.

Animal Data

A reproduction study has been performed in pregnant rabbits at single intravenous doses up to 100 mg/kg administered on gestation Day 7 (about 20 times the recommended human dosage) and has revealed no evidence of impaired fertility or harm to the fetus due to vedolizumab. A pre- and post-natal development study in monkeys showed no evidence of any adverse effect on pre- and post-natal development at intravenous doses up to 100 mg/kg (about 20 times the recommended human dosage).

8.2 Lactation

Risk Summary

Data from a clinical lactation study show the presence of vedolizumab in human milk. The mean calculated daily infant dosage was 0.02 mg/kg/day orally (see Data). Systemic exposure in a breastfed infant is expected to be low because monoclonal antibodies are largely degraded in the gastrointestinal tract. There are no data on the effects of vedolizumab on the breastfed infant, or the effects on milk production. The developmental and health benefits of breastfeeding should be considered along with the mother's clinical need for ENTYVIO and any potential adverse effects on the breastfed infant from ENTYVIO or from the underlying maternal condition.

Data

A milk-only lactation study was conducted in 9 adult lactating women being treated for active ulcerative colitis or Crohn's disease with intravenous ENTYVIO every 8 weeks after reaching steady state and completing the induction phase (ENTYVIO administration at 0, 2, and 6 weeks). Mean concentrations of ENTYVIO in human milk ranged from 0.03 to 0.26 mcg/mL. The mean calculated daily infant oral dosage was 0.02 mg/kg/day calculated as a product of the average concentration over the 8-week dosing interval and the standardized milk consumption of 150 mL/kg/day.

8.4 Pediatric Use

Safety and effectiveness of ENTYVIO in pediatric patients have not been established.

8.5 Geriatric Use

Clinical trials of ENTYVIO did not include sufficient numbers of patients aged 65 and over (72 patients with Crohn's disease or ulcerative colitis aged 65 and over were treated with ENTYVIO during controlled Phase 3 trials) to determine whether they respond differently from younger adult patients. However, no overall differences in safety or effectiveness were observed between these patients and younger adult patients, and other reported clinical experience has not identified differences in responses between the elderly and younger patients.

11 DESCRIPTION

Vedolizumab, an integrin receptor antagonist, is a humanized IgG1 monoclonal antibody produced in Chinese hamster ovary cells that binds to the human α4β7 integrin. ENTYVIO has an approximate molecular weight of 147 kilodaltons.

Intravenous ENTYVIO

ENTYVIO (vedolizumab) for injection is supplied as a sterile, white to off-white, preservative-free, lyophilized cake for intravenous infusion. After reconstitution with 4.8 mL Sterile Water for Injection, USP, 0.9% Sodium Chloride Injection, USP, or Lactated Ringer's Injection, USP, the resulting concentration is 60 mg/mL with a deliverable volume of 5 mL (300 mg) and the resulting pH is approximately 6.3.

Each single-dose vial contains 300 mg vedolizumab, arginine hydrochloride (131.7 mg), histidine (23 mg), histidine monohydrochloride (21.4 mg), polysorbate 80 (3 mg), and sucrose (500 mg).

Subcutaneous ENTYVIO

ENTYVIO (vedolizumab) injection is supplied as a sterile, clear to moderately opalescent, colorless to slightly yellow, preservative-free solution for subcutaneous administration.

Each single-dose prefilled syringe or single-dose prefilled pen (ENTYVIO PEN) contains 108 mg vedolizumab, arginine hydrochloride (17.77 mg), citric acid monohydrate (0.18 mg), histidine (3.86 mg), histidine monohydrochloride (1.86 mg), polysorbate 80 (1.35 mg), sodium citrate dihydrate (4.71 mg) and Sterile Water for Injection, USP, at a pH of 6.5.

12 CLINICAL PHARMACOLOGY

12.1 Mechanism of Action

Vedolizumab is a humanized monoclonal antibody that specifically binds to the α4β7 integrin and blocks the interaction of α4β7 integrin with mucosal addressin cell adhesion molecule-1 (MAdCAM-1) and inhibits the migration of memory T-lymphocytes across the endothelium into inflamed gastrointestinal parenchymal tissue. Vedolizumab does not bind to or inhibit function of the α4β1 and αEβ7 integrins and does not antagonize the interaction of α4 integrins with vascular cell adhesion molecule-1 (VCAM-1).

The α4β7 integrin is expressed on the surface of a discrete subset of memory T-lymphocytes that preferentially migrate into the gastrointestinal tract. MAdCAM-1 is mainly expressed on gut endothelial cells and plays a critical role in the homing of T-lymphocytes to gut lymph tissue. The interaction of the α4β7 integrin with MAdCAM-1 has been implicated as an important contributor to the chronic inflammation that is a hallmark of ulcerative colitis and Crohn's disease.

12.2 Pharmacodynamics

In clinical trials with intravenous ENTYVIO at doses ranging from 0.2 to 10 mg/kg (which includes doses outside of the recommended dose), saturation of α4β7 receptors on subsets of circulating lymphocytes involved in gut-immune surveillance was observed.

In clinical trials with intravenous ENTYVIO at doses ranging from 0.2 to 10 mg/kg and 180 to 750 mg (which include doses outside of the recommended dose) in healthy subjects and in patients with ulcerative colitis or Crohn's disease, vedolizumab did not elevate neutrophils, basophils, eosinophils, B-helper and cytotoxic T-lymphocytes, total memory helper T-lymphocytes, monocytes or natural killer cells.

A reduction in gastrointestinal inflammation was observed in rectal biopsy specimens from Phase 2 ulcerative colitis patients exposed to ENTYVIO for four or six weeks compared to placebo control as assessed by histopathology.

In a study of 14 healthy subjects, ENTYVIO did not affect the CD4+ lymphocyte cell counts, CD8+ lymphocyte cell counts, or the CD4+:CD8+ ratios in the CSF [see Clinical Pharmacology (12.3)].

12.3 Pharmacokinetics

Similar pharmacokinetics were observed in ulcerative colitis and Crohn's disease patients administered 300 mg ENTYVIO as a 30-minute intravenous infusion on Weeks 0, 2, and 6, and then every eight weeks up to Week 52 (Table 3).

Table 3. Mean ± SD Vedolizumab Concentrations in Patients [Data from patients in UC Trials I and II and CD Trials I and III with pharmacokinetic data available; data from patients with anti-vedolizumab antibody were excluded.] with Ulcerative Colitis and Crohn's Disease
Patient Population | Weeks 0, 2, and 6 ENTYVIO 300 mg Intravenously | After Week 6 to 52 ENTYVIO 300 mg Intravenously Every 8 Weeks
Patient Population | Trough Serum Concentration at Week 6 (mcg/mL) | Trough Serum Concentration at Week 46 [Steady-state trough serum concentration.] (mcg/mL)
Ulcerative Colitis | 26.3 ± 12.9 (N=210) | 11.2 ± 7.2 (N=77)
Crohn's Disease | 27.4 ± 19.2 (N=198) | 13.0 ± 9.1 (N=72)

In ulcerative colitis and Crohn’s disease patients, administered 300 mg ENTYVIO as a 30-minute intravenous infusion on Weeks 0 and 2, followed by 108 mg ENTYVIO as a subcutaneous injection every 2 weeks starting from Week 6, the mean steady state serum trough concentrations were 35.8 mcg/mL (SD ± 15.2) and 31.4 mcg/mL (SD ± 14.7), respectively.

The bioavailability of vedolizumab following a 108 mg single-dose subcutaneous injection relative to a 300 mg single-dose intravenous infusion in healthy subjects was approximately 75%. Following a 108 mg single-dose subcutaneous injection in healthy subjects, the median Tmax was 7 days with a range of 3 to 14 days and the mean Cmax was 15.4 mcg/mL (SD ± 3.2).

Vedolizumab clearance depends on both linear and nonlinear pathways; the nonlinear clearance decreases with increasing concentrations. Population pharmacokinetic analyses indicated that the linear clearance was approximately 0.16 L/day, the serum half-life was approximately 26 days, and the distribution volume was approximately 5 L.

Vedolizumab was not detected in the cerebrospinal fluid (CSF) of 14 healthy subjects at five weeks after a single intravenous administration of 450 mg ENTYVIO (1.5 times the recommended dosage).

Specific Populations

Population pharmacokinetic analysis showed that the severity of disease state, body weight, prior treatment with TNF blocker therapy, age (18 to 78 years), serum albumin, coadministered immunomodulators (including azathioprine, 6-mercaptopurine, methotrexate), and coadministered aminosalicylates did not have a clinically meaningful effect on the pharmacokinetics of ENTYVIO.

Pharmacokinetics of vedolizumab in patients with renal or hepatic insufficiency have not been studied.

12.6 Immunogenicity

The observed incidence of anti-drug antibodies is highly dependent on the sensitivity and specificity of the assay. Differences in assay methods preclude meaningful comparisons of the incidence of anti-drug antibodies in the studies described below with the incidence of anti-drug antibodies in other studies, including those of ENTYVIO or of other vedolizumab products.

Adults Treated with Intravenous ENTYVIO

The incidence of anti-drug antibodies to intravenous ENTYVIO using a drug-tolerant electrochemiluminescence (ECL) method for patients in UC Trials I and II and CD Trials I and III who had continuous ENTYVIO treatment administered as an intravenous infusion for 52 weeks was 6% (86 out of 1,427 total ENTYVIO-treated patients). Of the 86 patients who tested positive for anti-vedolizumab antibodies, 20 patients were persistently positive (at two or more consecutive study visits) and 56 developed neutralizing antibodies to vedolizumab.

Among the ENTYVIO-treated patients who developed persistent anti-vedolizumab antibodies, 14/20 patients had serum vedolizumab trough concentrations that were markedly reduced or undetectable and 15/20 patients did not achieve clinical remission at Week 52 in UC Trials I and II and CD Trials I and III. Because of the low occurrence of persistent anti-vedolizumab antibodies (1%; 20/1,427), the effect of these antibodies on the safety and effectiveness of ENTYVIO in these studies has not been fully characterized.

Adults Treated with Subcutaneous ENTYVIO

The incidence of anti-drug antibodies to ENTYVIO using a drug-tolerant ECL method for patients in SC UC Trial and SC CD Trial who had continuous treatment for 52 weeks was 3.4% (13 out of 381 total patients treated with subcutaneous ENTYVIO). Of the 13 patients who tested positive for anti-vedolizumab antibodies, 7 patients were persistently positive (at two or more consecutive study visits) and 7 patients developed neutralizing antibodies to vedolizumab. Two of the 7 patients with Crohn’s disease and none of the 6 patients with ulcerative colitis who had positive anti-vedolizumab antibodies achieved clinical remission at Week 52. There is insufficient data to assess the effect of anti-drug antibodies on pharmacokinetics, effectiveness, and safety of ENTYVIO in the SC UC and SC CD trials.

13 NONCLINICAL TOXICOLOGY

13.1 Carcinogenesis, Mutagenesis, Impairment of Fertility

Long-term studies in animals have not been performed to evaluate the carcinogenic potential of vedolizumab. Studies to evaluate the possible impairment of fertility or mutagenic potential of vedolizumab have not been performed.

14 CLINICAL STUDIES

14.1 Clinical Studies in Ulcerative Colitis

Intravenous Administration

The safety and efficacy of intravenous ENTYVIO were evaluated in two randomized, double-blind, placebo-controlled trials (UC Trials I and II) in adult patients with moderately to severely active ulcerative colitis (UC) defined as Mayo score of 6 to 12 with endoscopy subscore of two or three. The Mayo score ranges from 0 to 12 and has four subscales that are each scored from zero (normal) to three (most severe): stool frequency, rectal bleeding, findings on endoscopy, and physician global assessment. An endoscopy subscore of two is defined by marked erythema, lack of vascular pattern, friability, and erosions; an endoscopy subscore of three is defined by spontaneous bleeding and ulceration.

Enrolled patients in the U.S. had over the previous five-year period an inadequate response or intolerance to immunomodulator therapy (i.e., azathioprine or 6-mercaptopurine) and/or an inadequate response, loss of response, or intolerance to a TNF blocker. Outside the U.S., prior treatment with corticosteroids was sufficient for entry if over the previous five-year period the patients were corticosteroid dependent (i.e., unable to successfully taper corticosteroids without a return of the symptoms of UC) or had an inadequate response or intolerance to corticosteroids.

Patients that had received natalizumab ever in the past, and patients that had received a TNF blocker in the past 60 days were excluded from enrollment. Concomitant use of natalizumab or a TNF blocker was not allowed.

UC Trial I - Intravenous

In UC Trial I, 374 patients were randomized in a double-blind fashion (3:2) to receive ENTYVIO 300 mg or placebo by intravenous infusion at Week 0 and Week 2. Efficacy assessments were at Week 6. Concomitant stable dosages of aminosalicylates, corticosteroids (prednisone dosage ≤30 mg/day or equivalent), and immunomodulators (azathioprine or 6-mercaptopurine) were permitted through Week 6.

At baseline, patients received corticosteroids (54%), immunomodulators (azathioprine or 6-mercaptopurine) (30%), and/or aminosalicylates (74%). Thirty-nine percent of patients had an inadequate response, loss of response, or intolerance to a TNF blocker therapy. Eighteen percent of patients had an inadequate response, inability to taper or intolerance to prior corticosteroid treatment only (i.e., had not received prior immunomodulators or TNF blockers). The median baseline Mayo score was 9 in the ENTYVIO group and 8 in the placebo group.

In UC Trial I, a greater percentage of patients treated with intravenous ENTYVIO compared to patients treated with placebo achieved clinical response at Week 6 (defined in Table 4). A greater percentage of patients treated with intravenous ENTYVIO compared to patients treated with placebo also achieved clinical remission at Week 6 (defined in Table 4). In addition, a greater percentage of patients treated with ENTYVIO had improvement of endoscopic appearance of the mucosa at Week 6 (defined in Table 4).

Table 4. Proportion of Patients Meeting Efficacy Endpoints at Week 6 (UC Trial I)
Endpoint | Placebo N=149 | ENTYVIO IV N=225 | p-value | Treatment Difference and 95% CI
Clinical Response [Clinical response: reduction in complete Mayo score of ≥3 points and ≥30% from baseline with an accompanying decrease in rectal bleeding subscore of ≥1 point or absolute rectal bleeding subscore of ≤1 point.] at Week 6 | 26% | 47% | <0.001 | 22% (12%, 32%)
Clinical Remission [Clinical remission: complete Mayo score of ≤2 points and no individual subscore >1 point.] at Week 6 | 5% | 17% | 0.001 | 12% (5%, 18%)
Improvement of Endoscopic Appearance of the Mucosa [Improvement of endoscopic appearance of the mucosa: Mayo endoscopy subscore of 0 (normal or inactive disease) or 1 (erythema, decreased vascular pattern, mild friability).] at Week 6 | 25% | 41% | 0.001 | 16% (6%, 26%)

UC Trial II - Intravenous

In order to be randomized to treatment in UC Trial II, patients had to have received intravenous ENTYVIO and be in clinical response at Week 6. Patients could have come from either UC Trial I or from a group who received ENTYVIO open-label.

In UC Trial II, 373 patients were randomized in a double-blind fashion (1:1:1) to one of the following regimens beginning at Week 6: intravenous ENTYVIO 300 mg every eight weeks, intravenous ENTYVIO 300 mg every four weeks or placebo every four weeks. Efficacy assessments were at Week 52. Concomitant aminosalicylates and corticosteroids were permitted through Week 52. Concomitant immunomodulators (azathioprine or 6-mercaptopurine) were permitted outside the U.S. but were not permitted beyond Week 6 in the U.S.

At Week 6, patients were receiving corticosteroids (61%), immunomodulators (azathioprine or 6-mercaptopurine) (32%), and aminosalicylates (75%). Thirty-two percent of patients had an inadequate response, loss of response or intolerance to a TNF blocker therapy. At Week 6, the median Mayo score was 8 in the ENTYVIO every eight week group, the ENTYVIO every four week group, and the placebo group. Patients who had achieved clinical response at Week 6 and were receiving corticosteroids were required to begin a corticosteroid-tapering regimen at Week 6.

In UC Trial II, a greater percentage of patients in groups treated with intravenous ENTYVIO as compared to placebo achieved clinical remission at Week 52, and maintained clinical response (clinical response at both Weeks 6 and 52) (Table 5). In addition, a greater percentage of patients in groups treated with intravenous ENTYVIO as compared to placebo were in clinical remission at both Weeks 6 and 52, and had improvement of endoscopic appearance of the mucosa at Week 52 (Table 5). In the subgroup of patients who achieved clinical response at Week 6 and were receiving corticosteroid medication at baseline, a greater proportion of patients in groups treated with intravenous ENTYVIO as compared to placebo discontinued corticosteroids and were in clinical remission at Week 52 (Table 5).

The ENTYVIO every four week dosing regimen did not demonstrate additional clinical benefit over the every eight dosing week regimen. The every four week dosing regimen is not the recommended dosing regimen [see Dosage and Administration (2.2)].

Table 5. Proportion of Patients Meeting Efficacy Endpoints at Week 52 [Patients must have achieved clinical response at Week 6 to continue into UC Trial II. This group includes patients that were not in clinical remission at Week 6.] (UC Trial II)
Endpoint | Placebo [The placebo group includes those patients who received ENTYVIO at Week 0 and Week 2 and were randomized to receive placebo from Week 6 through Week 52.] N=126 | ENTYVIO IV Every 8 Weeks N=122 | p-value | Treatment Difference and 95% CI
Clinical Remission at Week 52 | 16% | 42% | <0.001 | 26% (15%, 37%)
Clinical Response at both Weeks 6 and 52 | 24% | 57% | <0.001 | 33% (21%, 45%)
Improvement of Endoscopic Appearance of the Mucosa [Improvement of endoscopic appearance of the mucosa: Mayo endoscopy subscore of 0 (normal or inactive disease) or 1 (erythema, decreased vascular pattern, mild friability) at Week 52.] at Week 52 | 20% | 52% | <0.001 | 32% (20%, 44%)
Clinical Remission at both Weeks 6 and 52 | 9% | 21% | 0.008 | 12% (3%, 21%)
Corticosteroid-free Clinical Remission [Corticosteroid-free clinical remission: Assessed in the subgroup of patients who were receiving corticosteroids at baseline and who were in clinical response at Week 6 (n=72 for placebo and n=70 for ENTYVIO every eight weeks). Corticosteroid-free clinical remission was defined as the proportion of patients in this subgroup that discontinued corticosteroids by Week 52 and were in clinical remission at Week 52.] | 14% | 31% | 0.012 | 18% (4%, 31%)

Subcutaneous Administration

SC UC Trial - Subcutaneous

The safety and efficacy of subcutaneous ENTYVIO was evaluated in a randomized, double-blind, placebo-controlled trial (SC UC Trial; NCT02611830) in adult patients with moderately to severely active ulcerative colitis defined as Mayo score of 6 to 12 with endoscopy subscore of two or three. The baseline Mayo score was between 9 to 12 in about 62% and six to eight in about 38% of the overall trial population.

The trial included patients who had experienced an inadequate response to, loss of response to, or intolerance to at least one of the following: at least one 12-week regimen of azathioprine or 6-mercaptopurine, induction with a TNF blocker, or corticosteroids. Patients were permitted to use concomitant stable doses of oral aminosalicylates, oral corticosteroids (prednisone ≤30 mg/day or budesonide ≤9 mg/day), azathioprine or 6-mercaptopurine, probiotics and/or antidiarrheals. Concomitant biologic therapies, rectal treatment with 5-aminosalicylic acid or corticosteroid enemas/suppositories were prohibited.

All patients received open-label intravenous ENTYVIO 300 mg at Week 0 and Week 2. In order to be randomized to treatment in SC UC Trial, patients had to be in clinical response at Week 6. A total of 162 patients were randomized at Week 6 in a double-blind fashion (2:1) to ENTYVIO 108 mg administered by subcutaneous injection or placebo every 2 weeks. Efficacy assessments were at Week 52.

Beginning at Week 6, patients who were receiving corticosteroids were required to begin a corticosteroid tapering regimen.

At the time of randomization into the double-blind phase (Week 6), patients were receiving corticosteroids (51%), immunomodulators (azathioprine or 6-mercaptopurine) (33%), and aminosalicylates (80%). Thirty-seven percent of patients had an inadequate response, loss of response, or intolerance to a TNF blocker therapy prior to enrollment.

Patients in the double-blind phase had a mean age of 39 years (range 18 to 69 years); 61% were male; 83% identified as White, 17% as Asian, and <1% identified as another racial group.

The primary endpoint was the proportion of patients in clinical remission defined as a Mayo score of ≤2 points and no individual subscore >1 point at Week 52. Secondary endpoints included the proportion of patients with improvement of endoscopic appearance of the mucosa at Week 52 and clinical response at both Weeks 6 and 52 (see Table 6).

Table 6. Proportion of Patients Meeting Efficacy Endpoints at Week 52 [Patients must have achieved clinical response at Week 6 to continue into SC UC Trial.] (SC UC Trial)
Endpoint | Placebo [The placebo group includes those subjects who received intravenous vedolizumab at Week 0 and Week 2 and were randomized to receive placebo from Week 6 through Week 52.] | ENTYVIO 108 mg SC Every 2 Weeks [Starting at Week 6 following two intravenous doses of ENTYVIO 300 mg administered as an intravenous infusion at Weeks 0 and 2.] | Estimate [Estimated treatment difference is based on the Cochran-Mantel-Haenszel method.] of Treatment Difference vs. Placebo (95% CI)
Clinical Remission [Clinical remission: Complete Mayo score of ≤2 points and no individual subscore >1 point at Week 52.] at Week 52
Total Population | N=56 14% | N=106 46% | 32 (20, 45) [p <0.001]
Prior TNF blocker failure | N=20 10% | N=40 35%
Without prior TNF blocker failure | N=36 17% | N=66 53%
Improvement of Endoscopic Appearance of the Mucosa at Week 52 [Improvement of endoscopic appearance of the mucosa: Mayo endoscopic subscore of ≤1 point.]
Total Population | N=56 21% | N=106 57% | 36 (22, 49)
Prior TNF blocker failure | N=20 10% | N=40 48%
Without prior TNF blocker failure | N=36 28% | N=66 62%
Clinical Response at both Weeks 6 and 52 [Clinical response: reduction in complete Mayo score of ≥3 points and ≥30% from baseline with an accompanying decrease in rectal bleeding subscore of ≥1 point or absolute rectal bleeding subscore of ≤1 point.]
Total Population | N=56 29% | N=106 64% | 36 (21, 51)
Prior TNF blocker failure | N=20 20% | N=40 68%
Without prior TNF blocker failure | N=36 33% | N=66 62%

Maintenance of remission at Week 52 in the subgroup of patients who were in remission at Week 6, was 64% (16/25) in the ENTYVIO-treated group compared to 20% (3/15) in the placebo group. The treatment difference was 44% (95% CI: 9%, 69%).

14.2 Clinical Studies in Crohn's Disease

Intravenous Administration

The safety and efficacy of intravenous ENTYVIO were evaluated in three randomized, double-blind, placebo-controlled clinical trials (CD Trials I, II, and III) in adult patients with moderately to severely active Crohn's disease (CD) (Crohn's Disease Activity Index [CDAI] score of 220 to 450).

Enrolled patients in the U.S. had over the previous five-year period an inadequate response or intolerance to immunomodulator therapy (i.e., azathioprine, 6-mercaptopurine, or methotrexate) and/or an inadequate response, loss of response, or intolerance to one or more TNF blockers. Outside the U.S., prior treatment with corticosteroids was sufficient for entry if over the previous five-year period the patients were corticosteroid dependent (i.e., unable to successfully taper corticosteroids without a return of the symptoms of CD) or had an inadequate response or intolerance to corticosteroids.

Patients that had received natalizumab ever in the past, and patients that had received a TNF blocker in the past 30 to 60 days were excluded from enrollment. Concomitant use of natalizumab or a TNF blocker was not allowed.

CD Trial I - Intravenous

In CD Trial I, 368 patients were randomized in a double-blind fashion (3:2) to receive ENTYVIO 300 mg or placebo by intravenous infusion at Week 0 and Week 2. Efficacy assessments were at Week 6. Concomitant stable dosages of aminosalicylates, corticosteroids (prednisone dosage ≤30 mg/day or equivalent), and immunomodulators (azathioprine, 6-mercaptopurine or methotrexate) were permitted through Week 6.

At baseline, patients were receiving corticosteroids (49%), immunomodulators (azathioprine, 6-mercaptopurine, or methotrexate) (35%), and/or aminosalicylates (46%). Forty-eight percent of the patients had an inadequate response, loss of response, or intolerance to a TNF blocker therapy. Seventeen percent of patients had inadequate response, inability to taper, or intolerance to prior corticosteroid treatment only (i.e., had not received prior immunomodulators or TNF blockers). The median baseline CDAI score was 324 in the intravenous ENTYVIO group and 319 in the placebo group.

In CD Trial I, a statistically significantly higher percentage of patients treated with intravenous ENTYVIO achieved clinical remission (defined as CDAI ≤150) as compared to placebo at Week 6 (Table 7). The difference in the percentage of patients who demonstrated clinical response (defined as a ≥100-point decrease in CDAI score from baseline), was however, not statistically significant at Week 6.

CD Trial II - Intravenous

Compared to CD Trial I, CD Trial II enrolled a higher number of patients who had over the previous five-year period had an inadequate response, loss of response, or intolerance to one or more TNF blockers (76%); this was the primary analysis population. In CD Trial II, 416 patients were randomized in a double-blind fashion (1:1) to receive either intravenous ENTYVIO 300 mg or placebo at Weeks 0, 2, and 6. Efficacy assessments were at Weeks 6 and 10. Concomitant aminosalicylates, corticosteroids, and immunomodulators (azathioprine, 6-mercaptopurine, or methotrexate) were permitted through Week 10.

At baseline, patients were receiving corticosteroids (54%), immunomodulators (azathioprine, 6-mercaptopurine, or methotrexate) (34%), and aminosalicylates (31%). The median baseline CDAI score was 317 in the ENTYVIO group and 301 in the placebo group.

For the primary endpoint (clinical remission at Week 6), treatment with intravenous ENTYVIO did not result in statistically significant improvement over placebo (Table 7). Secondary endpoints including assessments at Week 10 were not tested because the primary endpoint was not statistically significant.

Table 7. Proportion of Patients in Clinical Remission at Week 6 (CD Trials I and II)
Endpoint | Placebo | ENTYVIO IV | p-value | Treatment Difference and 95% CI
CD Trial I: Clinical Remission [Clinical Remission: CDAI ≤150.] at Week 6 | 7% (10/148) | 15% (32/220) | 0.041 [Adjusted p-value for multiple comparisons of two primary endpoints.] | 8% (1%, 14%)
CD Trial II [The primary analysis population for CD Trial II was patients that had an inadequate response, loss of response, or intolerance to one or more TNF blockers (76% of the overall population).] : Clinical Remission at Week 6 | 12% (19/157) | 15% (24/158) | NS [NS: Not significant (Secondary endpoints including assessments at Week 10 were not tested because the CD Trial II primary endpoint was not statistically significant).] | 3% (-5%, 11%)

CD Trial III - Intravenous

In order to be randomized to treatment in CD Trial III, patients had to have received intravenous ENTYVIO and be in clinical response (defined as a ≥70-point decrease in CDAI score from baseline) at Week 6. Patients could have come from either CD Trial I or from a group who received intravenous ENTYVIO open-label.

In CD Trial III, 461 patients were randomized in a double-blind fashion (1:1:1) to one of the following regimens beginning at Week 6: intravenous ENTYVIO 300 mg every eight weeks, intravenous ENTYVIO 300 mg every four weeks or placebo every four weeks. Efficacy assessments were at Week 52. Concomitant aminosalicylates and corticosteroids were permitted through Week 52. Concomitant immunomodulators (azathioprine, 6-mercaptopurine, or methotrexate) were permitted outside the U.S. but were not permitted beyond Week 6 in the U.S.

At Week 6, patients were receiving corticosteroids (59%), immunomodulators (azathioprine, 6-mercaptopurine, or methotrexate) (31%), and aminosalicylates (41%). Fifty-one percent of patients had an inadequate response, loss of response, or intolerance to a TNF blocker therapy. At Week 6, the median CDAI score was 322 in the intravenous ENTYVIO every eight week group, 316 in the intravenous ENTYVIO every four week group, and 315 in the placebo group. Patients who had achieved clinical response (≥70 decrease in CDAI score from baseline) at Week 6 and were receiving corticosteroids were required to begin a corticosteroid-tapering regimen at Week 6.

In CD Trial III a greater percentage of patients in groups treated with intravenous ENTYVIO as compared to placebo were in clinical remission (defined as CDAI score ≤150) at Week 52. A greater percentage of patients in groups treated with intravenous ENTYVIO as compared to placebo had a clinical response (defined as ≥100 decrease in CDAI score from baseline) at Week 52 (Table 8). In the subgroup of patients who were receiving corticosteroids at baseline and who were in clinical response at Week 6 (defined as ≥70 decrease in CDAI score from baseline), a greater proportion of patients in groups treated with intravenous ENTYVIO as compared to placebo discontinued corticosteroids by Week 52 and were in clinical remission at Week 52 (Table 8).

The ENTYVIO every four week dosing regimen did not demonstrate additional clinical benefit over the every eight dosing week regimen. The every four week dosing regimen is not the recommended dosing regimen [see Dosage and Administration (2.2)].

Table 8. Proportion of Patients Meeting Efficacy Endpoints at Week 52 [This group includes patients that were not in clinical remission at Week 6. Patients must have achieved clinical response (defined as ≥70 decrease in CDAI from baseline) at Week 6 to continue into CD Trial III.] (CD Trial III)
Endpoint | Placebo [The placebo group includes those patients who received ENTYVIO at Week 0 and Week 2, and were randomized to receive placebo from Week 6 through Week 52.] N=153 | ENTYVIO IV Every 8 Weeks N=154 | p-value | Treatment Difference and 95% CI
Clinical Remission [Clinical remission: CDAI ≤150.] at Week 52 | 22% | 39% | 0.001 | 17% (7%, 28%)
Clinical Response [Clinical response: ≥100 decrease in CDAI from baseline.] at Week 52 | 30% | 44% | 0.013 | 13% (3%, 24%)
Corticosteroid-free Clinical Remission [Corticosteroid-free clinical remission: Assessed in the subgroup of patients who were receiving corticosteroids at baseline and who were in clinical response (defined as ≥70 decrease in CDAI from baseline) at Week 6 (n=82 for placebo and n=82 for ENTYVIO every eight weeks). Corticosteroid-free clinical remission was defined as the proportion of patients in this subgroup that discontinued corticosteroids by Week 52 and were in clinical remission at Week 52.] | 16% | 32% | 0.015 | 16% (3%, 29%)

Subcutaneous Administration

SC CD Trial - Subcutaneous

The safety and efficacy of subcutaneous ENTYVIO was evaluated in a randomized, double-blind, placebo-controlled trial (SC CD Trial; NCT02611817) in adult patients with moderately to severely active Crohn’s disease defined as CDAI score of 220 to 450. At baseline, the median CDAI score was 316 (range: 198 to 559).

The trial included patients who had experienced an inadequate response to, loss of response to, or intolerance to at least one of the following: corticosteroids, immunomodulators (azathioprine, 6-mercaptopurine, or methotrexate), or TNF blockers (including primary non-responders). Patients were permitted to use concomitant stable doses of oral aminosalicylates, oral corticosteroids (prednisone ≤30 mg/day, budesonide ≤9 mg/day, or equivalent steroid), immunomodulators, probiotics, antidiarrheals, and/or antibiotics. Concomitant biologic therapies, rectal treatment with 5-aminosalicylic acid or corticosteroid enemas/suppositories were prohibited.

All patients received open-label intravenous ENTYVIO 300 mg at Week 0 and Week 2. In order to be randomized to treatment in SC CD Trial, patients had to be in clinical response (defined as a ≥70-point decrease in the CDAI score from baseline) at Week 6. A total of 409 patients were randomized at Week 6 in a double-blind fashion (2:1) to ENTYVIO 108 mg administered by subcutaneous injection or placebo every 2 weeks. Efficacy assessments were at Week 52.

Beginning at Week 6, patients who were receiving corticosteroids were required to begin a corticosteroid tapering regimen.

At the time of randomization into the double-blind phase (Week 6), patients were receiving corticosteroids (45%), immunomodulators (32%), and aminosalicylates (45%). Fifty-one percent of patients had an inadequate response, loss of response, or intolerance to a TNF blocker therapy prior to enrollment.

Patients in the double-blind phase had a mean age of 38 years (range 18 to 76 years); 55% were male; 91% identified as White, 6% as Asian, and 3% identified as another racial group.

The primary endpoint was the proportion of patients with clinical remission (CDAI score ≤150) at Week 52 (see Table 9).

Table 9. Proportion of Patients in Clinical Remission at Week 52 [Patients must have achieved clinical response at Week 6 to continue into SC CD Trial.] (SC CD Trial)
Endpoint | Placebo [The placebo group includes those subjects who received intravenous vedolizumab at Week 0 and Week 2, and were randomized to receive placebo from Week 6 through Week 52.] | ENTYVIO SC 108 mg Every 2 Weeks | Estimate [Estimate of treatment difference and the p-value are based on the Cochran-Mantel-Haenszel method.] of Treatment Difference (95% CI) Vedolizumab SC vs. Placebo
Clinical Remission [Clinical remission: CDAI score ≤150, at Week 52.] at Week 52
Total Population | N=134 34% | N=275 48% | 14 (4, 24) [p <0.01]
Prior TNF blocker failure /exposure | N=71 27% | N=168 48%
Without prior TNF blocker failure /exposure | N=63 43% | N=107 49%

Among patients using oral corticosteroids at baseline (Week 0) and achieving clinical response at Week 6, 45% (43/95) treated with subcutaneous ENTYVIO compared to 18% (8/44) treated with placebo discontinued corticosteroids and were in clinical remission at Week 52. This result was not statistically significant under the prespecified multiple testing procedure.

16 HOW SUPPLIED/STORAGE AND HANDLING

How Supplied

Intravenous Infusion

ENTYVIO® (vedolizumab) for injection for intravenous infusion is supplied in sterile single-dose glass vials, containing 300 mg of vedolizumab as a white to off-white lyophilized cake.

- ENTYVIO: 300 mg single-dose vial in individual carton: NDC 64764-300-20

Subcutaneous Injection

ENTYVIO (vedolizumab) injection for subcutaneous use is available in a prefilled syringe or a prefilled pen as a clear to moderately opalescent and colorless to slightly yellow solution.

The single-dose, disposable ENTYVIO prefilled syringe and single-dose, disposable ENTYVIO prefilled pen (ENTYVIO PEN) are comprised of a 1 mL long glass syringe with a fixed 27 gauge thin wall, ½ inch needle. The syringe has a rubber needle cover encased in a plastic shell and rubber stopper. Not made with natural rubber latex.

- ENTYVIO: 108 mg/0.68 single-dose prefilled syringe in an individual carton: NDC 64764-107-11
- ENTYVIO PEN: 108 mg/0.68 single-dose prefilled pen in an individual carton: NDC 64764-108-21

Storage and Handling

- Refrigerate ENTYVIO unopened vials, prefilled syringes, and prefilled pens at 2°C to 8°C (36° to 46°F).
- If needed, the ENTYVIO prefilled syringe or ENTYVIO PEN can be left out of the refrigerator in the original package at room temperature up to 25°C (77°F) for up to 7 days (for example, when traveling). Do not use ENTYVIO prefilled syringe or ENTYVIO PEN if left out of the refrigerator for more than 7 days.
- Do not freeze ENTYVIO vial, prefilled syringe, or prefilled pen. Do not use ENTYVIO vial, prefilled syringe, or prefilled pen if it has been frozen.
- Do not shake the ENTYVIO prefilled syringe or ENTYVIO PEN.
- Retain in original package to protect from light until the time of use.

17 PATIENT COUNSELING INFORMATION

Advise the patient to read the FDA-approved patient labeling (Medication Guide and Instructions for Use).

Infusion-Related and Hypersensitivity Reactions

Instruct patients to report immediately if they experience symptoms consistent with a hypersensitivity reaction during or following an infusion of ENTYVIO [see Warnings and Precautions (5.1)].

Infections

Inform patients that they may be more likely to develop infections when taking ENTYVIO. Instruct patients to tell their healthcare provider if they develop any signs or symptoms of an infection [see Warnings and Precautions (5.2)].

Progressive Multifocal Leukoencephalopathy

Inform patients that progressive multifocal leukoencephalopathy (PML) has occurred in patients who received some integrin receptor antagonist and systemic immunosuppressant products. Instruct patients to report if they experience any new onset or worsening of neurological signs and symptoms immediately, as these could be indicative of PML [see Warnings and Precautions (5.3)].

Liver Injury

Inform patients that elevated transaminase levels with or without elevated bilirubin has occurred in patients who received ENTYVIO. Instruct patients to report promptly any symptoms that may indicate liver injury, including fatigue, anorexia, right upper abdominal discomfort, dark urine or jaundice [see Warnings and Precautions (5.4)].

Subcutaneous Dosing Technique

Provide guidance to patients and caregivers on proper subcutaneous administration technique, and how to use the ENTYVIO single-dose prefilled syringe, or ENTYVIO single-dose prefilled pen correctly [see Instructions for Use].

Manufactured by:
Takeda Pharmaceuticals U.S.A., Inc.
Cambridge, MA 02142

U.S. License No. 1898

ENTYVIO is a registered trademark of Millennium Pharmaceuticals Inc. and is used under license by Takeda Pharmaceuticals U.S.A., Inc.
All other trademark names are the property of their respective owners.
©2024 Takeda Pharmaceuticals U.S.A., Inc.
VMB245 R14

MEDICATION GUIDE

ENTYVIO® (en ti' vee oh)
(vedolizumab)
for injection, for intravenous use

ENTYVIO® (en ti' vee oh)
(vedolizumab)
injection, for subcutaneous use

ENTYVIO® (en ti' vee oh) PEN
(vedolizumab)
injection, for subcutaneous use

What is the most important information I should know about ENTYVIO?
ENTYVIO may cause serious side effects, including:

- Infusion-related and serious allergic reactions. These reactions can happen while you are receiving ENTYVIO or several hours after treatment. You may need treatment if you have an allergic reaction. Tell your healthcare provider or get medical help right away if you get any of these symptoms during or after an infusion of ENTYVIO: rash, itching, swelling of your lips, tongue, throat or face, shortness of breath or trouble breathing, wheezing, dizziness, feeling hot, or palpitations (feel like your heart is racing).
- Infections. ENTYVIO may increase your risk of getting a serious infection. Before receiving ENTYVIO and during treatment with ENTYVIO, tell your healthcare provider if you think you have an infection or have symptoms of an infection such as fever, chills, muscle aches, cough, shortness of breath, runny nose, sore throat, red or painful skin or sores on your body, tiredness, or pain during urination.
- Progressive Multifocal Leukoencephalopathy (PML). People with weakened immune systems can get progressive multifocal leukoencephalopathy (PML) (a rare, serious brain infection caused by a virus). Although unlikely while receiving ENTYVIO, a risk of PML cannot be ruled out. PML can result in death or severe disability. There is no known treatment, prevention, or cure for PML. Tell your healthcare provider right away if you have any of the following symptoms: confusion or problems thinking, loss of balance, change in the way you walk or talk, decreased strength or weakness on one side of the body, blurred vision, or loss of vision.
- Liver Problems. Liver problems can happen in people who receive ENTYVIO. Tell your healthcare provider right away if you have any of the following symptoms: tiredness, loss of appetite, pain on the right side of your stomach (abdomen), dark urine, or yellowing of the skin and eyes (jaundice).

See "What are the possible side effects of ENTYVIO?" for more information about side effects.

What is ENTYVIO?
ENTYVIO is a prescription medicine used in adults for the treatment of:

- moderately to severely active ulcerative colitis (UC).
- moderately to severely active Crohn's disease (CD).

It is not known if ENTYVIO is safe and effective in children under 18 years of age.

Who should not receive ENTYVIO?
Do not receive ENTYVIO if you have had an allergic reaction to ENTYVIO or any of the ingredients in ENTYVIO. See the end of this Medication Guide for a complete list of ingredients in ENTYVIO.

Before receiving ENTYVIO, tell your healthcare provider about all of your medical conditions, including if you:

- have an infection, think you may have an infection or have infections that keep coming back (see "What is the most important information I should know about ENTYVIO?").
- have liver problems.
- have tuberculosis (TB) or have been in close contact with someone with TB.
- have recently received or are scheduled to receive a vaccine. Talk to your healthcare provider about bringing your vaccines up-to-date before starting treatment with ENTYVIO.
- are pregnant or plan to become pregnant. It is not known if ENTYVIO will harm your unborn baby. Tell your healthcare provider right away if you become pregnant while receiving ENTYVIO.
- are breastfeeding or plan to breastfeed. ENTYVIO can pass into your breast milk. Talk to your healthcare provider about the best way to feed your baby if you take ENTYVIO.

Tell your healthcare provider about all the medicines you take, including prescription and over-the-counter medicines, vitamins and herbal supplements.
Especially tell your healthcare provider if you take or have recently taken Tysabri (natalizumab), Tyruko (natalizumab-sztn), a Tumor Necrosis Factor (TNF) blocker medicine, a medicine that weakens your immune system (immunosuppressant), or corticosteroid medicine.

How should I use ENTYVIO?
When given in a vein (intravenously):

- You may receive ENTYVIO through a needle placed in a vein (intravenous infusion) in your arm.
  - ENTYVIO is given to you over a period of about 30 minutes.
  - Your healthcare provider will monitor you during and after the ENTYVIO infusion for side effects to see if you have a reaction to the treatment.

When given under the skin (subcutaneously):

- You may receive ENTYVIO as an injection under your skin (subcutaneous) every 2 weeks. You may receive your first subcutaneous injection after at least 2 intravenous infusions in place of the next scheduled intravenous infusion.
  - See the detailed Instructions for Use that comes with ENTYVIO about the right way to prepare and give ENTYVIO.
  - ENTYVIO is provided as single-dose prefilled syringe or single-dose prefilled pen (ENTYVIO PEN) for subcutaneous use. Your healthcare provider will prescribe the type that is best for you.
  - If your healthcare provider decides that you or your caregiver can give your injections of ENTYVIO at home, you or your caregiver should be shown the right way to prepare and inject ENTYVIO.
  - Do not inject ENTYVIO until you or your caregiver have been shown the right way by your healthcare provider.
  - Always check the label of your prefilled syringe or prefilled pen to make sure you have the correct medicine before each injection.
  - Do not shake ENTYVIO.
  - ENTYVIO is injected under your skin (subcutaneously) 1 time every 2 weeks.
  - Inject ENTYVIO under the skin (subcutaneous injection) in your upper legs (thighs) or stomach area (abdomen). The upper arms may also be used if a caregiver gives the injection.
  - Use a different injection site each time you use ENTYVIO.
  - Do not give an injection into moles, scars, bruises, or skin that is tender, hard, red, or damaged.
  - If you are not able to inject ENTYVIO at your regular scheduled time or you miss a dose of ENTYVIO, inject the dose as soon as possible. Then, inject your next dose every 2 weeks thereafter. If you are not sure when to inject ENTYVIO, call your healthcare provider.
  - If you take more ENTYVIO than you were told to take, call your healthcare provider.

What are the possible side effects of ENTYVIO?
ENTYVIO may cause serious side effects, see "What is the most important information I should know about ENTYVIO?"
The most common side effects of ENTYVIO include: common cold, headache, joint pain, nausea, fever, infections of the nose and throat, tiredness, cough, bronchitis, flu, back pain, rash, itching, sinus infection, throat pain, pain in extremities, and with injections under the skin: pain, swelling, itching, hives, bruising, rash, or redness at the injection site.
These are not all of the possible side effects of ENTYVIO.
Call your doctor for medical advice about side effects. You may report side effects to FDA at 1-800-FDA-1088.

How should I store ENTYVIO?

- Store ENTYVIO in a refrigerator between 36°F to 46°F (2°C to 8°C).
- If needed, the prefilled syringe or prefilled pen can be left out of the refrigerator in its box at room temperature up to 77°F (25°C) for up to 7 days (for example, when traveling). Do not use the prefilled syringe or prefilled pen if left out of the refrigerator for more than 7 days or left in direct sunlight.
- Do not freeze ENTYVIO. Do not use ENTYVIO if it has been frozen.
- Keep ENTYVIO in the original package to protect from light until the time of use.
- ENTYVIO prefilled syringe or prefilled pen is not made with natural rubber latex.

Keep ENTYVIO and all medicines out of the reach of children.

General information about the safe and effective use of ENTYVIO.
Medicines are sometimes prescribed for purposes other than those listed in a Medication Guide. Do not use ENTYVIO for a condition for which it was not prescribed. Do not give ENTYVIO to other people, even if they have the same symptoms that you have. It may harm them. You can ask your pharmacist or healthcare provider for information about ENTYVIO that is written for health professionals.

What are the ingredients in ENTYVIO?
Active ingredient: vedolizumab
Inactive ingredients in vial for intravenous infusion: arginine hydrochloride, histidine, histidine monohydrochloride, polysorbate 80 and sucrose
Inactive ingredients in prefilled syringe or prefilled pen for subcutaneous injection: arginine hydrochloride, citric acid monohydrate, histidine, histidine monohydrochloride, polysorbate 80, sodium citrate dihydrate, and Sterile Water for Injection
Manufactured by: Takeda Pharmaceuticals U.S.A., Inc.
Cambridge, MA 02142
U.S. License No. 1898
ENTYVIO is a registered trademark of Millennium Pharmaceuticals Inc. and is used under license by Takeda Pharmaceuticals U.S.A., Inc.
All other trademark names are the property of their respective owners.
©2024 Takeda Pharmaceuticals U.S.A., Inc.
For more information, go to www.ENTYVIO.com or call 1-877-TAKEDA7 (1-877-825-3327).

This Medication Guide has been approved by the U.S. Food and Drug Administration

VMB245 R11 Revised: 5/2024

INSTRUCTIONS FOR USE

ENTYVIO® (en ti' vee oh) PEN
(vedolizumab)
injection, for subcutaneous use
Single-dose prefilled pen

This Instructions for Use contains information on how to inject ENTYVIO.

Your ENTYVIO single-dose prefilled pen

Important information you need to know before injecting ENTYVIO:

- Read and follow this Instructions for Use before you inject ENTYVIO.
- Your healthcare provider should show you how to use the ENTYVIO PEN before you use it for the first time.
- ENTYVIO PEN is for subcutaneous injection only (inject directly into fatty layer under the skin).
- Do not shake the prefilled pen.
- Do not remove the purple cap from the prefilled pen until you are ready to inject.
- Do not put or press your thumb, fingers, or hand over the yellow needle shield. The yellow needle shield is visible when the purple cap is removed.
- Do not use the prefilled pen if it is dropped or damaged.

Storing ENTYVIO

- Store your prefilled pen in the refrigerator between 36°F to 46°F (2°C to 8°C).
- Your prefilled pen can be left in its box at room temperature up to 77°F (25°C) for up to 7 days (for example, when traveling). Do not use the prefilled pen if it is left out of the refrigerator for more than 7 days.
- Do not freeze the prefilled pen.
- Do not leave the prefilled pen in direct sunlight.
- Throw away the prefilled pen in a FDA-cleared sharps disposal container if it has been left out of the refrigerator for more than 7 days, frozen, or left in direct sunlight. See Step 14 for instructions on how to throw away (dispose of) the prefilled pen.
- Always keep ENTYVIO PENs, the sharps disposal container, and all medicines out of the reach of children.

Getting Your Supplies Ready

Step 1. Remove the ENTYVIO PEN box from the refrigerator

Take 1 prefilled pen box from the refrigerator and check the expiration date on the box (see Figure A).

- Do not use the prefilled pen if any of the seals on the box are broken.
- Do not use the prefilled pen if the expiration date on the box has passed.

Figure A

Step 2. Wait 30 minutes

Wait 30 minutes and let the prefilled pen come to room temperature (see Figure B).

- Do not warm the prefilled pen any other way.
- Do not let the prefilled pen sit in direct sunlight.
- Do not take the prefilled pen out of its tray until you are ready to inject.

Figure B

Step 3. Gather supplies

Find a clean, flat surface like a table. Gather supplies that are not in the prefilled pen box (see Figure C).

- Alcohol pad
- Cotton ball or gauze
- Sharps disposal container (see Step 14 "Throw away (dispose of) the prefilled pen")

Figure C

Preparing to Inject ENTYVIO

Step 4. Wash hands

Wash your hands with soap and clean water (see Figure D).

Figure D

Step 5. Remove the prefilled pen from the tray

Peel off the paper on the tray and lift the prefilled pen straight out (see Figure E).

- Do not shake the prefilled pen.
- Do not remove the purple cap from the prefilled pen until Step 9.

Figure E

Step 6. Inspect the prefilled pen

Check the expiration date (EXP) printed on the prefilled pen and the medicine in the prefilled pen viewing window (see Figure F). The medicine should be colorless to pale yellow. It is normal to see air bubbles. Inspect the prefilled pen for any damage.

- Do not use the prefilled pen if the expiration date on the prefilled pen has passed.
- Do not use the prefilled pen if the medicine is cloudy or has particles floating in it.
- Do not use the prefilled pen if any part of it is damaged.

Step 7. Choose injection site

Choose an injection site on your bare skin from one of the following (see Figure G):

- front of the thighs
- stomach area (avoid the area 2 inches around the belly button)
  For caregivers only: back of the upper arms may also be used.

- Do not inject into the same spot you used for your last injection.
- Do not inject into moles, scars, bruises, or skin that is tender, hard, red, or damaged.

Figure G

Step 8. Clean the injection site

Clean the injection site with an alcohol pad (see Figure H). Let your skin dry.

- Do not touch or blow on the cleaned injection site before you inject.

Figure H

Continue to Step 9 ➔

Injecting ENTYVIO

Step 9. Remove the purple cap and throw it away

When you are ready to inject, pull the purple cap straight off and throw it right away in the sharps disposal container (see Figure I).

- The needle is inside the yellow needle shield (under purple cap).
- Do not put or press your thumb, fingers, or hand over the yellow needle shield.
- Do not put the purple cap back on. This could accidentally start the injection.

Figure I

Step 10. Place the prefilled pen on the injection site

- Hold the prefilled pen so you can see the viewing window.
- Place the yellow end of the prefilled pen flat on your skin at 90 degrees to the injection site (see Figure J).
- The needle is inside the yellow needle shield.
- Do not push down on the prefilled pen until you are ready to inject.

Figure J

Step 11. Start injecting ENTYVIO

Step 12. Complete injecting ENTYVIO

Push the prefilled pen straight down and hold for at least 10 seconds (see Figure K).

- You may hear a first click when the injection starts.
- You may hear a second click. This is not the end of the injection.
- Continue holding the prefilled pen with constant pressure and watch the window turn purple.

Continue holding the prefilled pen with constant pressure until the viewing window has filled with purple to make sure you have received your full dose (see Figure L).

- You will see a small amount of gray in the viewing window. This is normal.
- If the viewing window did not fill with purple, you may not have received your full dose. Call your pharmacy or healthcare provider.

Step 13. Lift prefilled pen from skin

Lift the prefilled pen from the injection site (see Figure M). The yellow needle shield will drop down and lock over the needle.

- When you remove the prefilled pen, if the window has not turned purple, or it looks like the medicine is still coming out of the prefilled pen, this means you have not received a full dose. Call your pharmacy or healthcare provider right away.
- You may see a small amount of blood at the injection site. If you do, press on your skin with a cotton ball or gauze.

Figure M

Step 14. Throw away (dispose of) the prefilled pen

Throw away (dispose of) the used prefilled pen in a FDA-cleared sharps disposal container right away after use (see Figure N). Do not recycle or throw away the prefilled pen in your household trash.

- Throw away the remaining supplies in your household trash or sharps disposal container.
- If you do not have a FDA-cleared sharps disposal container, you may use a household container that is:
  - made of heavy-duty plastic,
  - can be closed with a tight-fitting, puncture-resistant lid, without sharps being able to come out,
  - upright and stable during use,
  - leak-resistant, and
  - properly labeled to warn of hazardous waste inside the container.
- When your sharps disposal container is almost full, you will need to follow your community guidelines for the right way to dispose of your sharps disposal container. There may be local or state laws about how you should throw away needles and syringes.
- For more information about safe sharps disposal, and for specific information about sharps disposal in the state you live in, go to the FDA's website at: http://www.fda.gov/safesharpsdisposal.

If you have questions or concerns about your ENTYVIO PEN, please call your healthcare provider. You can also call 877-825-3327 or visit www.ENTYVIO.com for more information.
Manufactured by:
Takeda Pharmaceuticals U.S.A., Inc.
Cambridge, MA 02142

Figure N

U.S. License No. 1898

This Instructions for Use has been approved by the U.S. Food and Drug Administration.
Revised: 5/2024

INSTRUCTIONS FOR USE

ENTYVIO® (en ti' vee oh)
(vedolizumab)
injection, for subcutaneous use
Single-dose prefilled syringe

This Instructions for Use contains information on how to inject ENTYVIO.

Your ENTYVIO single-dose prefilled syringe

Important information you need to know before injecting ENTYVIO:

- Read and follow this Instructions for Use before you inject ENTYVIO.
- Your healthcare provider should show you how to use the ENTYVIO prefilled syringe before you use it for the first time.
- ENTYVIO prefilled syringe is for subcutaneous injection only (inject directly into fatty layer under the skin).
- Do not shake the prefilled syringe.
- Do not remove the needle cap from the prefilled syringe until you are ready to inject.
- Do not use the prefilled syringe if it is dropped or damaged.
- Each prefilled syringe has a needle guard. It will automatically cover the needle after the injection is completed to reduce the risk of accidental needle sticks.

Storing ENTYVIO

- Store your prefilled syringe in the refrigerator between 36°F to 46°F (2°C to 8°C).
- Your prefilled syringe can be left in its box at room temperature up to 77°F (25°C) for up to 7 days (for example, when traveling). Do not use the prefilled syringe if it is left out of the refrigerator for more than 7 days.
- Do not freeze the prefilled syringe.
- Do not leave the prefilled syringe in direct sunlight.
- Throw away the prefilled syringe in a FDA-cleared sharps disposal container if it has been left out of the refrigerator for more than 7 days, frozen, or left in direct sunlight. See Step 14 for instructions on how to throw away (dispose of) the prefilled syringe.
- Always keep ENTYVIO prefilled syringes, the sharps disposal container, and all medicines out of the reach of children.

Getting Your Supplies Ready

Step 1. Remove the ENTYVIO prefilled syringe box from the refrigerator

Take 1 prefilled syringe box from the refrigerator and check the expiration date on the box (see Figure A).

- Do not use the prefilled syringe if any of the seals on the box are broken.
- Do not use the prefilled syringe if the expiration date on the box has passed.

Figure A

Step 2. Wait 30 minutes

Wait 30 minutes and let the prefilled syringe come to room temperature (see Figure B).

- Do not warm the prefilled syringe any other way.
- Do not let the prefilled syringe sit in direct sunlight.
- Do not take the prefilled syringe out of its tray until you are ready to inject.

Figure B

Step 3. Gather supplies

Find a clean, flat surface like a table. Gather supplies that are not in the prefilled syringe box (see Figure C).

- Alcohol pad
- Cotton ball or gauze
- Sharps disposal container (see Step 14 "Throw away (dispose of) the prefilled syringe")

Figure C

Preparing to Inject ENTYVIO

Step 4. Wash hands

Wash your hands with soap and clean water (see Figure D).

Figure D

Step 5. Remove the prefilled syringe from the tray

Peel off the paper on the tray and lift the prefilled syringe straight out (see Figure E).

- Do not lift from the purple plunger.
- Do not shake the prefilled syringe.
- Do not remove the needle cap from the prefilled syringe until Step 9.

Figure E

Step 6. Inspect the prefilled syringe

Check the expiration date (EXP) printed on the prefilled syringe and the medicine in the prefilled syringe (see Figure F). The medicine should be colorless to pale yellow. It is normal to see air bubbles. Inspect the prefilled syringe for any damage.

- Do not use the prefilled syringe if the expiration date on the prefilled syringe has passed.
- Do not use the prefilled syringe if the medicine is cloudy or has particles floating in it.
- Do not use the prefilled syringe if any part of it is damaged.
- Do not try to remove air bubbles from the prefilled syringe.

Figure F

Step 7. Choose injection site

Choose an injection site on your bare skin from one of the following (see Figure G):

- front of the thighs
- stomach area (avoid the area 2 inches around the belly button)
  For caregivers only: back of the upper arms may also be used.

- Do not inject into the same spot you used for your last injection.
- Do not inject into moles, scars, bruises, or skin that is tender, hard, red, or damaged.

Figure G

Step 8. Clean the injection site

Clean the injection site with an alcohol pad (see Figure H). Let your skin dry.

- Do not touch or blow on the cleaned injection site before you inject.

Figure H

Continue to Step 9 ➔

Injecting ENTYVIO

Step 9. Remove the needle cap and throw it away

When you are ready to inject, pull the needle cap straight off and throw it right away in the sharps disposal container (see Figure I). You may see a drop of liquid at the end of the needle. This is normal.

- Do not touch or pull back the purple plunger.
- Do not touch or re-cap the needle.
- Do not use a prefilled syringe with a bent or broken needle.

Figure I

Step 10. Pinch the skin

With the needle cap off, hold the prefilled syringe with one hand and pinch the skin around the injection site with your other hand (see Figure J).

- Hold the pinch until the injection is completed.

Figure J

Step 11. Insert the prefilled syringe at 45-degree angle

Insert the needle at about a 45-degree angle all the way into the pinched skin (see Figure K).

- Avoid touching the plunger until the needle is inserted.

Figure K

Step 12. Push down on the plunger

Push the plunger all the way down until all the medicine is injected (see Figure L).

- Keep pressure on the plunger and take the needle out of the skin.
- If you are not able to start or cannot complete the injection by pushing the plunger all the way down, you may not have received your full dose. Call your pharmacy or healthcare provider.

Figure L

Step 13. Take your thumb off the plunger

Take your thumb off the plunger to allow the needle guard to cover the needle (see Figure M).

- You may see a small amount of blood at the injection site. If you do, press on your skin with a cotton ball or gauze.

Figure M

Step 14. Throw away (dispose of) the prefilled syringe

Throw away (dispose of) the used prefilled syringe in a FDA-cleared sharps disposal container right away after use (see Figure N). Do not recycle or throw away the prefilled syringe in your household trash.

- Throw away the remaining supplies in your household trash or sharps disposal container.
- If you do not have a FDA-cleared sharps disposal container, you may use a household container that is:
  - made of heavy-duty plastic,
  - can be closed with a tight-fitting, puncture-resistant lid, without sharps being able to come out,
  - upright and stable during use,
  - leak-resistant, and
  - properly labeled to warn of hazardous waste inside the container.
- When your sharps disposal container is almost full, you will need to follow your community guidelines for the right way to dispose of your sharps disposal container. There may be local or state laws about how you should throw away needles and syringes.
- For more information about safe sharps disposal, and for specific information about sharps disposal in the state you live in, go to the FDA's website at: http://www.fda.gov/safesharpsdisposal.

If you have questions or concerns about your ENTYVIO prefilled syringe, please call your healthcare provider. You can also call 877-825-3327 or visit www.ENTYVIO.com for more information.
Manufactured by:
Takeda Pharmaceuticals U.S.A., Inc.
Cambridge, MA 02142

Figure N

U.S. License No. 1898

This Instructions for Use has been approved by the U.S. Food and Drug Administration.
Revised: 5/2024

PRINCIPAL DISPLAY PANEL - 300 mg Vial Label

NDC 64764-300-20 Rx only

Entyvio
vedolizumab
for injection
300 mg per vial*

For Intravenous Use Only

Must be reconstituted
and diluted prior to use

Single-Dose Vial - Discard Unused
Portion

PRINCIPAL DISPLAY PANEL - 300 mg Vial Carton

NDC 64764-300-20 Rx only

Entyvio
vedolizumab
for injection
300 mg per vial*

ATTENTION: Each patient is required to
receive the enclosed Medication Guide.

For Intravenous Use Only

Must be reconstituted and diluted prior
to use

Single-Dose Vial - Discard Unused Portion

Takeda

PRINCIPAL DISPLAY PANEL - 108 mg/0.68 mL Pen Tray Carton

NDC 64764-108-21 Rx only

ENTYVIO® PEN
(vedolizumab)
injection

108 mg/0.68 mL

For Subcutaneous Use Only

1 Single-Dose Prefilled Pen

ATTENTION PHARMACIST: Each
patient is required to receive the
enclosed Medication Guide.

PRINCIPAL DISPLAY PANEL - 108 mg/0.68 mL Syringe Tray Carton

NDC 64764-107-11 Rx only

ENTYVIO®
(vedolizumab)
injection

108 mg/0.68 mL

For Subcutaneous Use Only

1 Single-Dose Prefilled Syringe

ATTENTION PHARMACIST: Each patient
is required to receive the enclosed
Medication Guide.